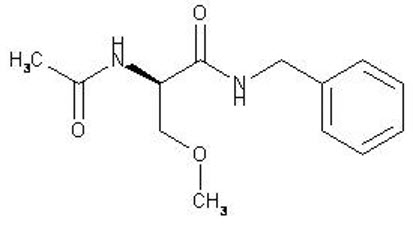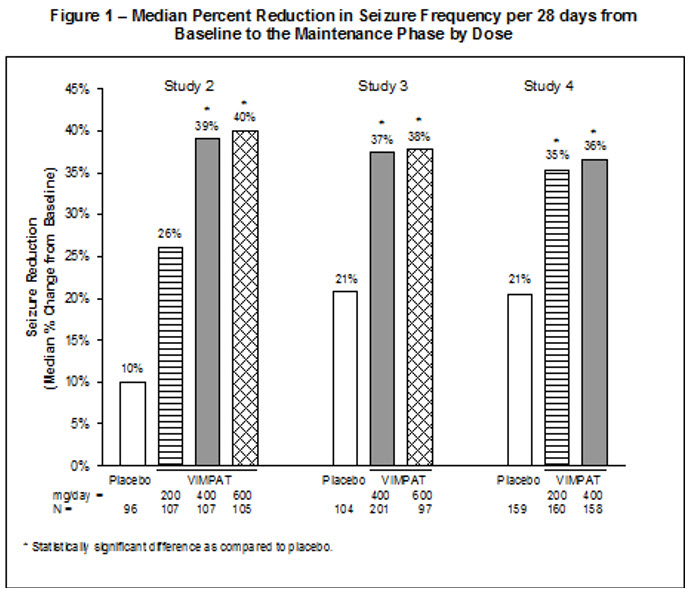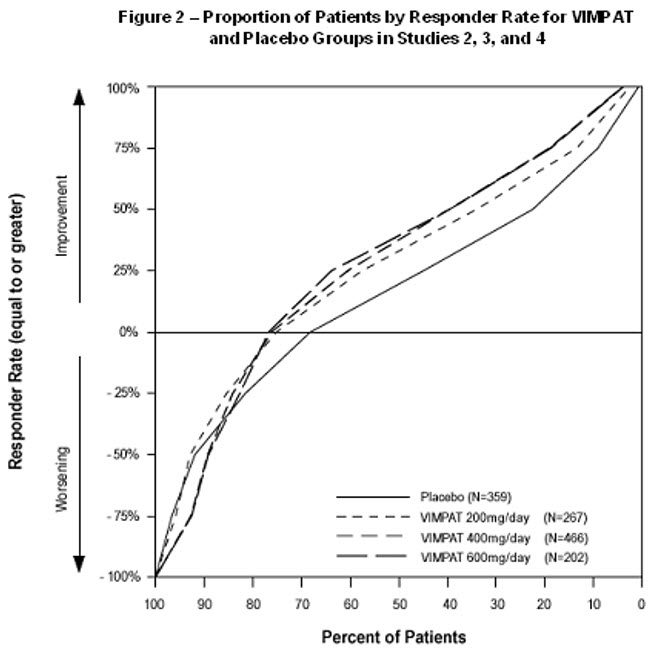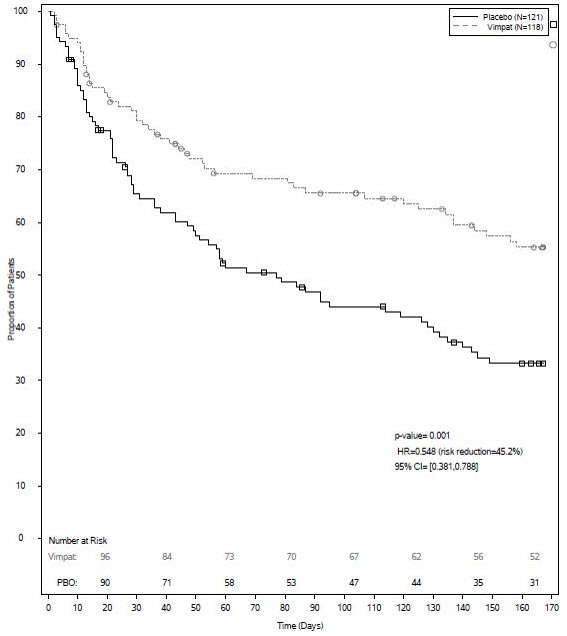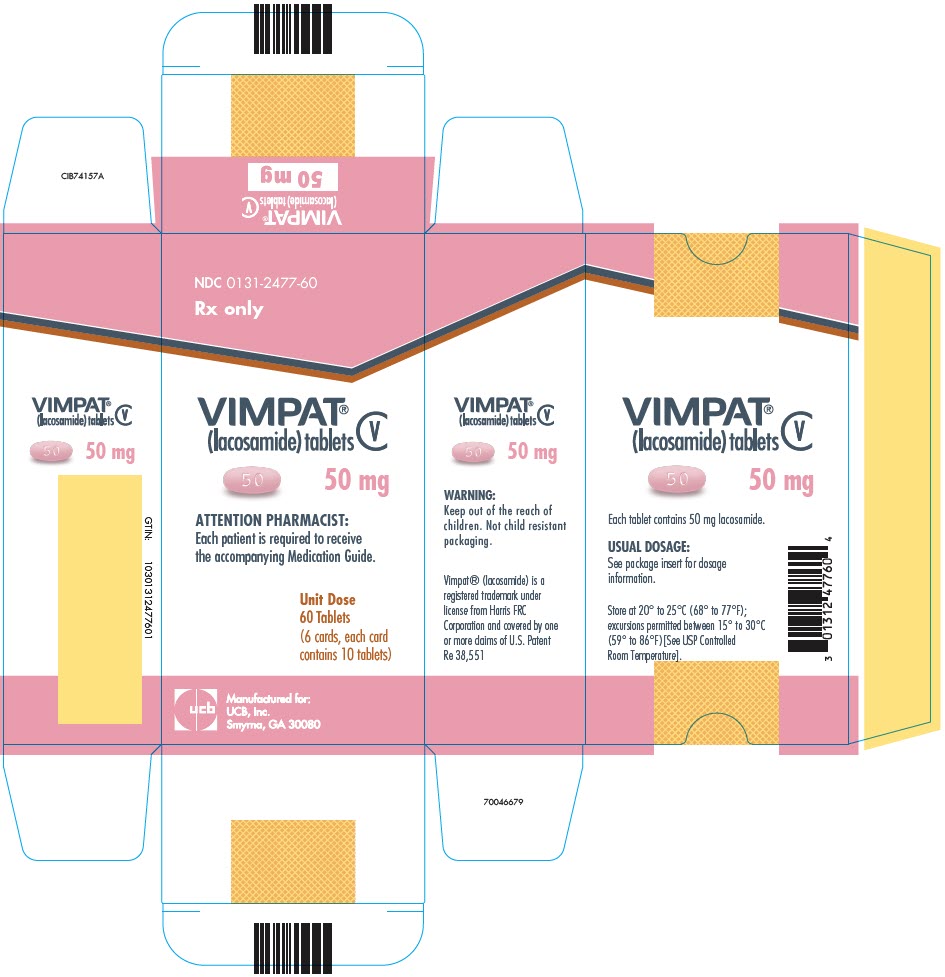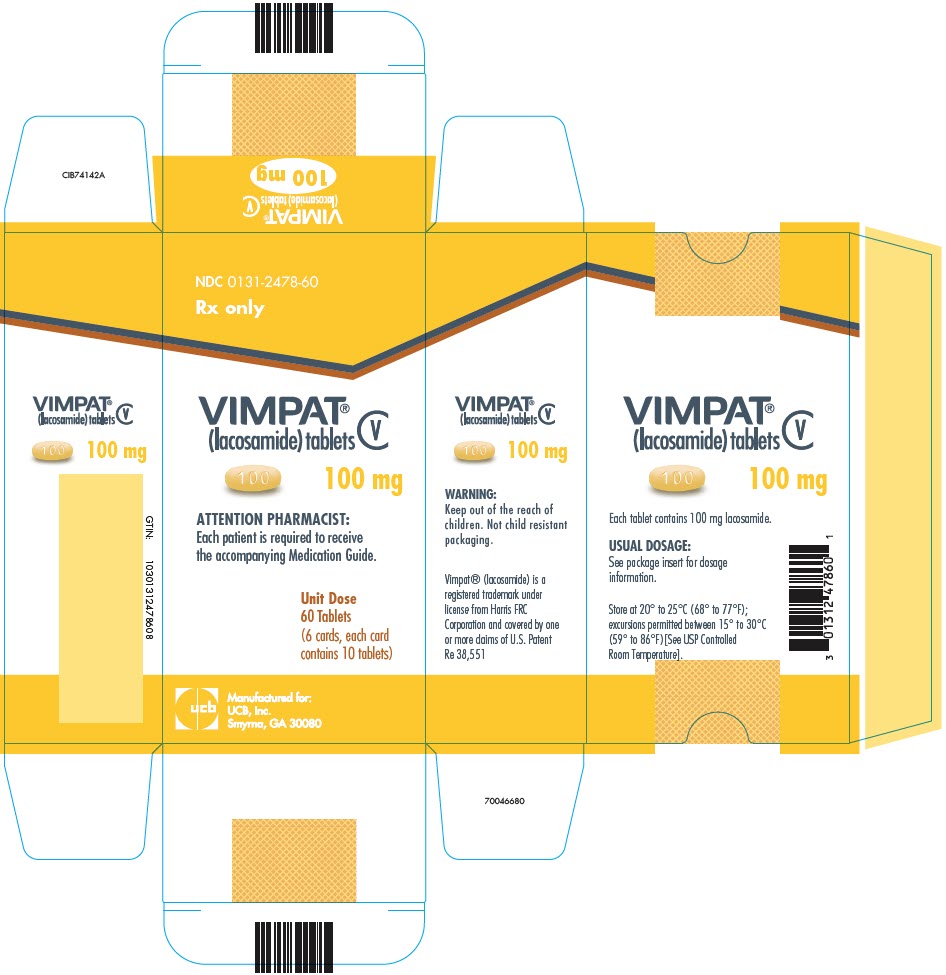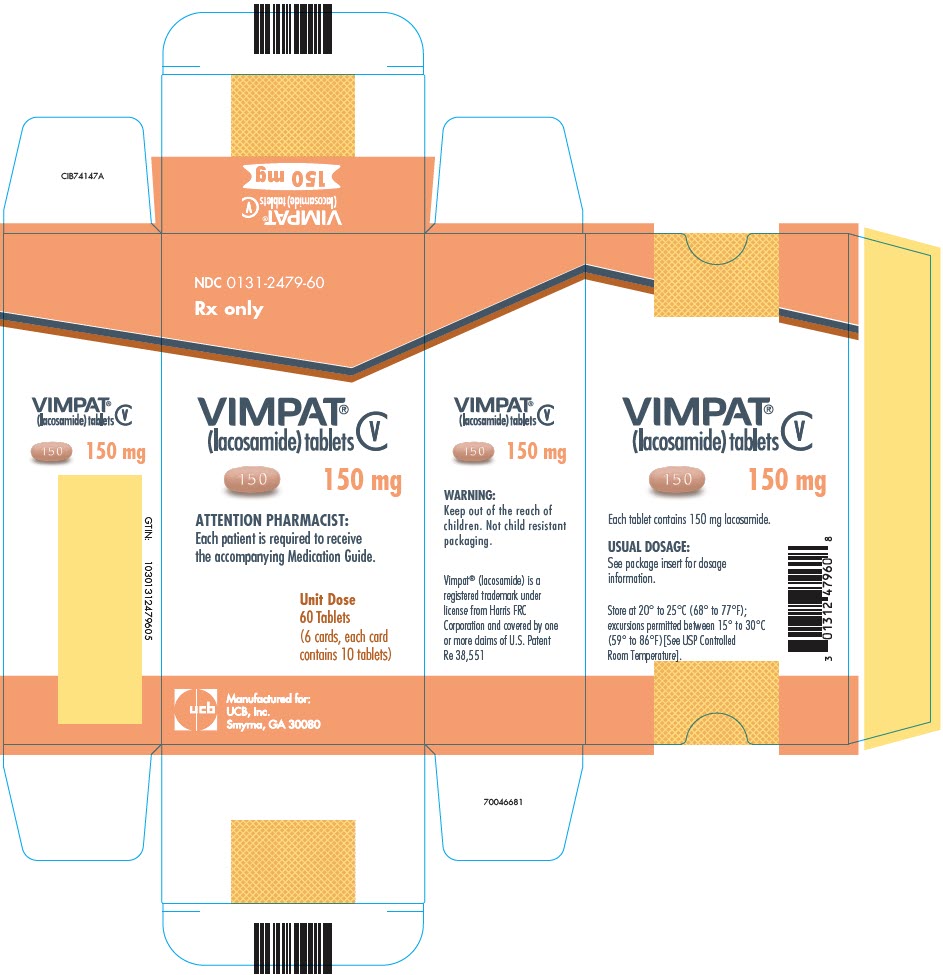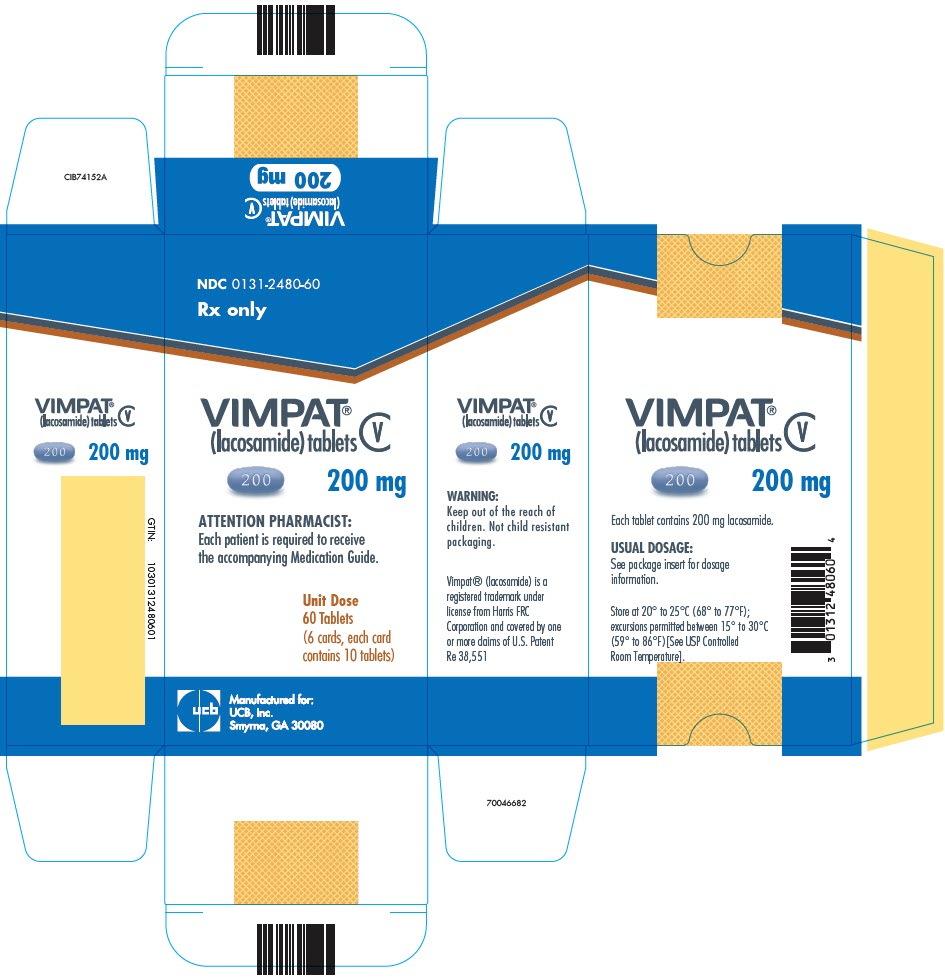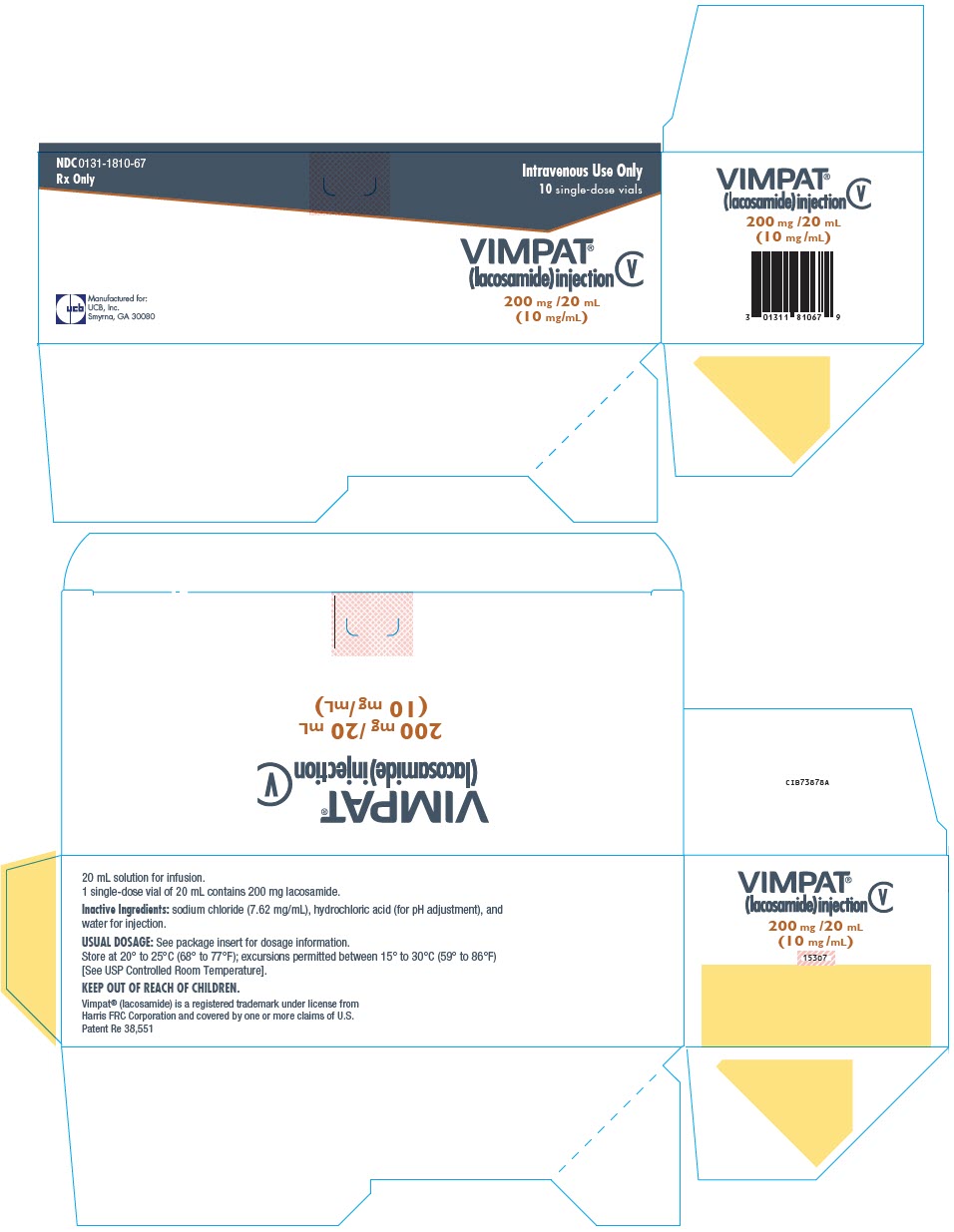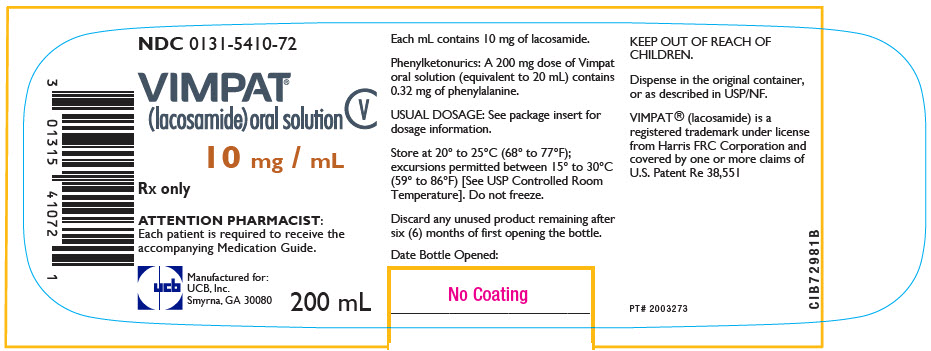 DRUG LABEL: Vimpat
NDC: 0131-2477 | Form: TABLET, FILM COATED
Manufacturer: UCB, Inc.
Category: prescription | Type: HUMAN PRESCRIPTION DRUG LABEL
Date: 20250820
DEA Schedule: CV

ACTIVE INGREDIENTS: LACOSAMIDE 50 mg/1 1
INACTIVE INGREDIENTS: SILICON DIOXIDE; CROSPOVIDONE (120 .MU.M); HYDROXYPROPYL CELLULOSE (1600000 WAMW); MAGNESIUM STEARATE; MICROCRYSTALLINE CELLULOSE; POLYETHYLENE GLYCOL, UNSPECIFIED; POLYVINYL ALCOHOL, UNSPECIFIED; TALC; TITANIUM DIOXIDE; FERRIC OXIDE RED; FERROSOFERRIC OXIDE; FD&C BLUE NO. 2; ALUMINUM OXIDE; INDIGOTINDISULFONATE SODIUM

HIGHLIGHTS OF PRESCRIBING INFORMATION

These highlights do not include all the information needed to use VIMPAT®safely and effectively. See full prescribing information for VIMPAT.
VIMPAT®(lacosamide) film coated tablet, for oral use, CV
VIMPAT®(lacosamide) injection, for intravenous use, CV
VIMPAT®(lacosamide) oral solution, CV
Initial U.S. Approval: 2008

RECENT MAJOR CHANGES

Dosage and Administration (2.1) | 4/2023
Dosage and Administration (2.2) | 10/2023

1 INDICATIONS AND USAGE

VIMPAT is indicated for:

- Treatment of partial-onset seizures in patients 1 month of age and older (1.1)
- Adjunctive therapy in the treatment of primary generalized tonic-clonic seizures in patients 4 years of age and older (1.2)

2 DOSAGE AND ADMINISTRATION

- Adults (17 years and older):
  - Initial dosage for monotherapy for the treatment of partial-onset seizures is 100 mg twice daily (2.1)
  - Initial dosage for adjunctive therapy for the treatment of partial-onset seizures or primary generalized tonic-clonic seizures is 50 mg twice daily (2.1)
  - Maximum recommended dosage for monotherapy and adjunctive therapy is 200 mg twice daily (2.1)
- Pediatric Patients 1 month to less than 17 years: The recommended dosage is based on body weight and is administered orally twice daily (2.1)
- Increase dosage based on clinical response and tolerability, no more frequently than once per week (2.1)
- Injection: for intravenous use only when oral administration is temporarily not feasible; the recommended dosage is based on body weight and is administered two or three times daily over 15 to 60 minutes; obtaining ECG before initiation is recommended in certain patients (2.7, 5.3)
- Dose adjustment is recommended for severe renal impairment (2.4, 12.3)
- Dose adjustment is recommended for mild or moderate hepatic impairment; use in patients with severe hepatic impairment is not recommended (2.5, 12.3)

3 DOSAGE FORMS AND STRENGTHS

- 50 mg, 100 mg, 150 mg, 200 mg tablets (3)
- 200 mg/20 mL single-dose vial for intravenous use (3)
- 10 mg/mL oral solution (3)

4 CONTRAINDICATIONS

None (4)

5 WARNINGS AND PRECAUTIONS

- Monitor patients for suicidal behavior and ideation (5.1)
- VIMPAT may cause dizziness and ataxia (5.2)
- Cardiac Rhythm and Conduction Abnormalities: Obtaining ECG before beginning and after titration to steady-state maintenance is recommended in patients with underlying proarrhythmic conditions or on concomitant medications that affect cardiac conduction; closely monitor these patients (5.3, 7.2)
- VIMPAT may cause syncope (5.4)
- VIMPAT should be gradually withdrawn to minimize the potential of increased seizure frequency (5.5)
- Drug Reaction with Eosinophilia and Systemic Symptoms (DRESS)/ Multi-Organ Hypersensitivity: Discontinue if no alternate etiology (5.6)

6 ADVERSE REACTIONS

- Adjunctive therapy: Most common adverse reactions in adults (≥10% and greater than placebo) are diplopia, headache, dizziness, nausea, and somnolence (6.1)
- Monotherapy: Most common adverse reactions are similar to those seen in adjunctive therapy studies (6.1)
- Pediatric patients: Adverse reactions are similar to those seen in adult patients (6.1)

To report SUSPECTED ADVERSE REACTIONS, contact UCB, Inc. at 1-844-599-2273 or FDA at 1-800-FDA-1088 or www.fda.gov/medwatch

8 USE IN SPECIFIC POPULATIONS

- Pregnancy: Based on animal data, may cause fetal harm (8.1)

FULL PRESCRIBING INFORMATION

1 INDICATIONS AND USAGE

1.1 Partial-Onset Seizures

VIMPAT is indicated for the treatment of partial-onset seizures in patients 1 month of age and older.

1.2 Primary Generalized Tonic-Clonic Seizures

VIMPAT is indicated as adjunctive therapy in the treatment of primary generalized tonic-clonic seizures in patients 4 years of age and older.

2 DOSAGE AND ADMINISTRATION

2.1 Dosage Information

The recommended dosage for monotherapy and adjunctive therapy for partial-onset seizures in patients 1 month of age and older and for adjunctive therapy for primary generalized tonic-clonic seizures in patients 4 years of age and older is included in Table 1. In pediatric patients, the recommended dosing regimen is dependent upon body weight. Dosage should be increased based on clinical response and tolerability, no more frequently than once per week. Titration increments should not exceed those shown in Table 1.

Table 1: Recommended Dosages for Partial-Onset Seizures (Monotherapy or Adjunctive Therapy) in Patients 1 Month and Older, and for Primary Generalized Tonic-Clonic Seizures (Adjunctive Therapy) in Patients 4 Years of Age and Older [when not specified, the dosage is the same for monotherapy for partial-onset seizures and adjunctive therapy for partial-onset seizures or primary generalized tonic-clonic seizures. Oral and intravenous dosages are the same unless specified.]
Age and Body Weight | Initial Dosage | Titration Regimen | Maintenance Dosage
Adults (17 years and older) | Monotherapy [Monotherapy for partial-onset seizures only] : 100 mg twice daily (200 mg per day) Adjunctive Therapy: 50 mg twice daily (100 mg per day) | Increase by 50 mg twice daily (100 mg per day) every week | Monotherapy : 150 mg to 200 mg twice daily (300 mg to 400 mg per day) Adjunctive Therapy: 100 mg to 200 mg twice daily (200 mg to 400 mg per day)
Adults (17 years and older) |  | Increase by 50 mg twice daily (100 mg per day) every week | Monotherapy : 150 mg to 200 mg twice daily (300 mg to 400 mg per day) Adjunctive Therapy: 100 mg to 200 mg twice daily (200 mg to 400 mg per day)
Pediatric patients weighing at least 50 kg | 50 mg twice daily (100 mg per day) | Increase by 50 mg twice daily (100 mg per day) every week | Monotherapy : 150 mg to 200 mg twice daily (300 mg to 400 mg per day) Adjunctive Therapy: 100 mg to 200 mg twice daily (200 mg to 400 mg per day)
Pediatric patients weighing 30 kg to less than 50 kg | 1 mg/kg twice daily (2 mg/kg/day) | Increase by 1 mg/kg twice daily (2 mg/kg/day) every week | 2 mg/kg to 4 mg/kg twice daily (4 mg/kg/day to 8 mg/kg/day)
Pediatric patients weighing 11 kg to less than 30 kg | 1 mg/kg twice daily (2 mg/kg/day) | Increase by 1 mg/kg twice daily (2 mg/kg/day) every week | 3 mg/kg to 6 mg/kg twice daily (6 mg/kg/day to 12 mg/kg/day)
Pediatric patients weighing 6 kg to less than 11 kg [indicated only for partial-onset seizures] | 1 mg/kg twice daily (2 mg/kg/day) | Increase by 1 mg/kg twice daily (2 mg/kg/day) every week | 3 mg/kg to 6 mg/kg twice daily (6 mg/kg/day to 12 mg/kg/day)
Pediatric patients weighing less than 6 kg | Intravenous: 0.66 mg/kg three times daily (2 mg/kg/day) | Intravenous: Increase by 0.66 mg/kg three times daily (2 mg/kg/day) every week | Intravenous: 2.5 mg/kg to 5 mg/kg three times daily (7.5 mg/kg/day to 15 mg/kg/day)
Pediatric patients weighing less than 6 kg | Oral: 1 mg/kg twice daily (2 mg/kg/day) | Oral: Increase by 1 mg/kg twice daily (2 mg/kg/day) every week | Oral: 3.75 mg/kg to 7.5 mg/kg twice daily (7.5 mg/kg/day to 15 mg/kg/day)

In adjunctive clinical trials in adult patients with partial-onset seizures, a dosage higher than 200 mg twice daily (400 mg per day) was not more effective and was associated with a substantially higher rate of adverse reactions [see Adverse Reactions (6.1)and Clinical Studies (14.2)] .

VIMPAT Injection Dosage

VIMPAT injection may be used when oral administration is temporarily not feasible [see Dosage and Administration (2.6)and Warnings and Precautions (5.3)]. VIMPAT injection can be administered intravenously to adult and pediatric patients weighing 6 kg or more with the same dosing regimens described for oral dosing. For pediatric patients weighing less than 6 kg, VIMPAT injection may be initiated with a dose of 0.66 mg/kg three times daily (see Table 1).

The clinical study experience of intravenous VIMPAT is limited to 5 days of consecutive treatment.

2.2 Alternate Initial Dosage Information to Achieve the Maintenance Dosage in a Shorter Timeframe

For monotherapy and adjunctive therapy for partial-onset seizures in patients 1 month of age and older and for adjunctive therapy for primary generalized tonic-clonic seizures in patients 4 years of age and older, an alternate initial dosing regimen for week 1 (e.g., including a loading dose and/or a higher initial dosage) may be administered in patients for whom achieving the recommended maintenance dosage in a shorter timeframe is clinically indicated (see Table 2). The alternate initial dosage regimen should be continued for one week. VIMPAT may then be titrated based on clinical response and tolerability, no more frequently than once per week, if needed. The loading dose should be administered with medical supervision because of the possibility of increased incidence of adverse reactions, including central nervous system (CNS) and cardiovascular adverse reactions [see Warnings and Precautions (5.2, 5.3), Adverse Reactions (6.1), and Clinical Pharmacology (12.3)] . Titration increments should not exceed those shown in Table 2.

Table 2: Alternate Initial Dosing Regimen to Achieve the Maintenance Dosage in a Shorter Timeframe if Clinically Indicated [when not specified, the dosage is the same for monotherapy for partial-onset seizures and adjunctive therapy for partial-onset seizures or primary generalized tonic-clonic seizures. Oral and intravenous dosages are the same unless specified.]
Age and Body Weight | Alternate Initial Dosage | Titration Regimen | Maintenance Dosage
Adults (17 years and older) | Single loading dose: 200 mg 12 hours later initiate: 100 mg twice daily (200 mg per day) | Increase by 50 mg twice daily (100 mg per day) at weekly intervals, if needed | Monotherapy [Monotherapy for partial-onset seizures only] : 150 mg to 200 mg twice daily (300 mg to 400 mg per day) Adjunctive Therapy: 100 mg to 200 mg twice daily (200 mg to 400 mg per day)
Pediatric patients weighing at least 50 kg | Single loading dose: 200 mg 12 hours later initiate: 100 mg twice daily (200 mg per day) | Increase by 50 mg twice daily (100 mg per day) at weekly intervals, if needed | Monotherapy : 150 mg to 200 mg twice daily (300 mg to 400 mg per day) Adjunctive Therapy: 100 mg to 200 mg twice daily (200 mg to 400 mg per day)
Pediatric patients weighing 30 kg to less than 50 kg | Single loading dose: 4 mg/kg 12 hours later initiate: 2 mg/kg twice daily (4 mg/kg/day) | Increase by 1 mg/kg twice daily (2 mg/kg/day) at weekly intervals, if needed | 2 mg/kg to 4 mg/kg twice daily (4 mg/kg/day to 8 mg/kg/day)
Pediatric patients weighing 11 kg to less than 30 kg | Single loading dose: 4.5 mg/kg 12 hours later initiate: 3 mg/kg twice daily (6 mg/kg/day) | Increase by 1 mg/kg twice daily (2 mg/kg/day) at weekly intervals, if needed | 3 mg/kg to 6 mg/kg twice daily (6 mg/kg/day to 12 mg/kg/day)
Pediatric patients weighing 6 kg to less than 11 kg [indicated only for partial-onset seizures] | Single loading dose: 4.5 mg/kg 12 hours later initiate: 3 mg/kg twice daily (6 mg/kg/day) | Increase by 1 mg/kg twice daily (2 mg/kg/day) at weekly intervals, if needed | 3 mg/kg to 6 mg/kg twice daily (6 mg/kg/day to 12 mg/kg/day)
Pediatric patients weighing less than 6 kg | Intravenous: No loading dose required 2.5 mg/kg three times daily (7.5 mg/kg/day) | Intravenous: Increase by 0.66 mg/kg three times daily (2 mg/kg/day) at weekly intervals, if needed | Intravenous: 2.5 mg/kg to 5 mg/kg three times daily (7.5 mg/kg/day to 15 mg/kg/day)
Pediatric patients weighing less than 6 kg | Oral: No loading dose required 3.75 mg/kg twice daily (7.5 mg/kg/day) | Oral: Increase by 1 mg/kg twice daily (2 mg/kg/day) at weekly intervals, if needed | Oral: 3.75 mg/kg to 7.5 mg/kg twice daily (7.5 mg/kg/day to 15 mg/kg/day)

2.3 Converting From a Single Antiepileptic (AED) to VIMPAT Monotherapy for the Treatment of Partial-Onset Seizures

For patients who are already on a single AED and will convert to VIMPAT monotherapy, withdrawal of the concomitant AED should not occur until the therapeutic dosage of VIMPAT is achieved and has been administered for at least 3 days. A gradual withdrawal of the concomitant AED over at least 6 weeks is recommended.

2.4 Dosage Information for Patients with Renal Impairment

For patients with mild to moderate renal impairment, no dosage adjustment is necessary. For patients with severe renal impairment [creatinine clearance (CLCR) less than 30 mL/min as estimated by the Cockcroft-Gault equation for adults; CLCRless than 30 mL/min/1.73m^2as estimated by the Schwartz equation for pediatric patients] or end-stage renal disease, a reduction of 25% of the maximum dosage is recommended.

In all patients with renal impairment, dose initiation and titration should be based on clinical response and tolerability.

Hemodialysis

VIMPAT is effectively removed from plasma by hemodialysis. Following a 4-hour hemodialysis treatment, dosage supplementation of up to 50% should be considered.

Concomitant Strong CYP3A4 or CYP2C9 Inhibitors

Dose reduction may be necessary in patients with renal impairment who are taking strong inhibitors of CYP3A4 and CYP2C9 [see Drug Interactions (7.1), Use in Specific Populations (8.6), and Clinical Pharmacology (12.3)] .

2.5 Dosage Information for Patients with Hepatic Impairment

For patients with mild or moderate hepatic impairment, a reduction of 25% of the maximum dosage is recommended. The dose initiation and titration should be based on clinical response and tolerability in patients with hepatic impairment.

VIMPAT use is not recommended in patients with severe hepatic impairment.

Concomitant Strong CYP3A4 and CYP2C9 Inhibitors

Dose reduction may be necessary in patients with hepatic impairment who are taking strong inhibitors of CYP3A4 and CYP2C9 [see Drug Interactions (7.1), Use in Specific Populations (8.7), and Clinical Pharmacology (12.3)] .

2.6 Administration Instructions for VIMPAT Tablets and Oral Solution

VIMPAT tablets and oral solution may be taken with or without food.

VIMPAT Tablets

VIMPAT tablets should be swallowed whole with liquid. Do not divide VIMPAT tablets.

VIMPAT Oral Solution

A calibrated measuring device is recommended to measure and deliver the prescribed dose accurately. A household teaspoon or tablespoon is not an adequate measuring device.

VIMPAT oral solution may also be administered using a nasogastric tube or gastrostomy tube.

Discard any unused VIMPAT oral solution remaining after 6 months of first opening the bottle.

2.7 Preparation and Administration Information for VIMPAT Injection

Preparation

VIMPAT injection can be administered intravenously without further dilution or may be mixed with diluents listed below. The diluted solution should not be stored for more than 4 hours at room temperature.

Diluents:

Sodium Chloride Injection 0.9% (w/v)
Dextrose Injection 5% (w/v)
Lactated Ringer's Injection

Parenteral drug products should be inspected visually for particulate matter and discoloration prior to administration, whenever solution and container permit. Product with particulate matter or discoloration should not be used.

VIMPAT injection is for single-dose only. Any unused portion of VIMPAT injection should be discarded.

Administration

The recommended infusion duration is 30 to 60 minutes; however, infusions as rapid as 15 minutes can be administered in adults if required [see Adverse Reactions (6.1)and Clinical Pharmacology (12.3)]. Infusion durations less than 30 minutes are generally not recommended in pediatric patients [see Adverse Reactions (6.1)].

Intravenous infusion of VIMPAT may cause bradycardia, AV blocks, and ventricular tachyarrhythmia [see Warnings and Precautions (5.3)] . Obtaining an ECG before beginning VIMPAT and after VIMPAT is titrated to steady-state maintenance dose is recommended in patients with underlying proarrhythmic conditions or on concomitant medications that affect cardiac conduction [see Drug Interactions (7.2)] .

Storage and Stability

The diluted solution should not be stored for more than 4 hours at room temperature. Any unused portion of VIMPAT injection should be discarded.

2.8 Discontinuation of VIMPAT

When discontinuing VIMPAT, a gradual withdrawal over at least 1 week is recommended [see Warnings and Precautions (5.5)] .

3 DOSAGE FORMS AND STRENGTHS

VIMPAT Tablets

- 50 mg: pink, oval, film-coated, debossed with "SP" on one side and "50" on the other
- 100 mg: dark yellow, oval, film-coated, debossed with "SP" on one side and "100" on the other
- 150 mg: salmon, oval, film-coated, debossed with "SP" on one side and "150" on the other
- 200 mg: blue, oval, film-coated, debossed with "SP" on one side and "200" on the other

VIMPAT Injection

- 200 mg/20 mL: clear, colorless sterile solution in single-dose vials

VIMPAT Oral Solution

- 10 mg/mL: clear, colorless to yellow or yellow-brown, strawberry-flavored liquid

4 CONTRAINDICATIONS

None .

5 WARNINGS AND PRECAUTIONS

5.1 Suicidal Behavior and Ideation

Antiepileptic drugs (AEDs), including VIMPAT, increase the risk of suicidal thoughts or behavior in patients taking these drugs for any indication. Patients treated with any AED for any indication should be monitored for the emergence or worsening of depression, suicidal thoughts or behavior, and/or any unusual changes in mood or behavior.

Pooled analyses of 199 placebo-controlled clinical trials (mono- and adjunctive therapy) of 11 different AEDs showed that patients randomized to one of the AEDs had approximately twice the risk (adjusted Relative Risk 1.8, 95% CI:1.2, 2.7) of suicidal thinking or behavior compared to patients randomized to placebo. In these trials, which had a median treatment duration of 12 weeks, the estimated incidence of suicidal behavior or ideation among 27,863 AED-treated patients was 0.43%, compared to 0.24% among 16,029 placebo-treated patients, representing an increase of approximately one case of suicidal thinking or behavior for every 530 patients treated.There were four suicides in drug-treated patients in the trials and none in placebo-treated patients, but the number of events is too small to allow any conclusion about drug effect on suicide.

The increased risk of suicidal thoughts or behavior with AEDs was observed as early as one week after starting treatment with AEDs and persisted for the duration of treatment assessed. Because most trials included in the analysis did not extend beyond 24 weeks, the risk of suicidal thoughts or behavior beyond 24 weeks could not be assessed.

The risk of suicidal thoughts or behavior was generally consistent among drugs in the data analyzed. The finding of increased risk with AEDs of varying mechanisms of action and across a range of indications suggests that the risk applies to all AEDs used for any indication. The risk did not vary substantially by age (5-100 years) in the clinical trials analyzed.

Table 3 shows absolute and relative risk by indication for all evaluated AEDs.

Table 3: Risk by Indication for Antiepileptic Drugs in the Pooled Analysis
Indication | Placebo Patients with Events Per 1000 Patients | Drug Patients with Events Per 1000 Patients | Relative Risk: Incidence of Events in Drug Patients/Incidence in Placebo Patients | Risk Difference: Additional Drug Patients with Events Per 1000 Patients
Epilepsy | 1.0 | 3.4 | 3.5 | 2.4
Psychiatric | 5.7 | 8.5 | 1.5 | 2.9
Other | 1.0 | 1.8 | 1.9 | 0.9
Total | 2.4 | 4.3 | 1.8 | 1.9

The relative risk for suicidal thoughts or behavior was higher in clinical trials for epilepsy than in clinical trials for psychiatric or other conditions, but the absolute risk differences were similar.

Anyone considering prescribing VIMPAT or any other AED must balance this risk with the risk of untreated illness. Epilepsy and many other illnesses for which antiepileptics are prescribed are themselves associated with morbidity and mortality and an increased risk of suicidal thoughts and behavior. Should suicidal thoughts and behavior emerge during treatment, the prescriber needs to consider whether the emergence of these symptoms in any given patient may be related to the illness being treated.

5.2 Dizziness and Ataxia

VIMPAT may cause dizziness and ataxia in adult and pediatric patients. In adult patients with partial-onset seizures taking 1 to 3 concomitant AEDs, dizziness was experienced by 25% of patients randomized to the recommended doses (200 to 400 mg/day) of VIMPAT (compared with 8% of placebo patients) and was the adverse reaction most frequently leading to discontinuation (3%). Ataxia was experienced by 6% of patients randomized to the recommended doses (200 to 400 mg/day) of VIMPAT (compared to 2% of placebo patients). The onset of dizziness and ataxia was most commonly observed during titration. There was a substantial increase in these adverse reactions at doses higher than 400 mg/day [see Adverse Reactions (6.1)] . If a loading dose is clinically indicated, administer with medical supervision because of the possibility of increased incidence of adverse reactions, including CNS adverse reactions such as dizziness and ataxia.

5.3 Cardiac Rhythm and Conduction Abnormalities

PR Interval Prolongation, Atrioventricular Block, and Ventricular Tachyarrhythmia

Dose-dependent prolongations in PR interval with VIMPAT have been observed in clinical studies in adult patients and in healthy volunteers [see Clinical Pharmacology (12.2)] . In adjunctive clinical trials in adult patients with partial-onset seizures, asymptomatic first-degree atrioventricular (AV) block was observed as an adverse reaction in 0.4% (4/944) of patients randomized to receive VIMPAT and 0% (0/364) of patients randomized to receive placebo. One case of profound bradycardia was observed in a patient during a 15-minute infusion of 150 mg VIMPAT. When VIMPAT is given with other drugs that prolong the PR interval, further PR prolongation is possible.

In the postmarketing setting, there have been reports of cardiac arrhythmias in patients treated with VIMPAT, including bradycardia, AV block,and ventricular tachyarrhythmia, which have rarely resulted in asystole, cardiac arrest, and death. Most, although not all, cases have occurred in patients with underlying proarrhythmic conditions, or in those taking concomitant medications that affect cardiac conduction or prolong the PR interval. These events have occurred with both oral and intravenous routes of administration and at prescribed doses as well as in the setting of overdose [see Overdosage (10)] . In all patients for whom a loading dose is clinically indicated, administer the loading dose with medical supervision because of the possibility of increased incidence of adverse reactions, including cardiovascular adverse reactions.

VIMPAT should be used with caution in patients with underlying proarrhythmic conditions such as known cardiac conduction problems (e.g., marked first-degree AV block, second-degree or higher AV block and sick sinus syndrome without pacemaker), severe cardiac disease (such as myocardial ischemia or heart failure, or structural heart disease), and cardiac sodium channelopathies (e.g., Brugada Syndrome). VIMPAT should also be used with caution in patients on concomitant medications that affect cardiac conduction, including sodium channel blockers, beta-blockers, calcium channel blockers, potassium channel blockers, and medications that prolong the PR interval [see Drug Interactions (7.2)] . In such patients, obtaining an ECG before beginning VIMPAT, and after VIMPAT is titrated to steady-state maintenance dose, is recommended. In addition, these patients should be closely monitored if they are administered VIMPAT through the intravenous route [see Adverse Reactions (6.1)and Drug Interactions (7.2)].

Atrial Fibrillation and Atrial Flutter

In the short-term investigational trials of VIMPAT in adult patients with partial-onset seizures there were no cases of atrial fibrillation or flutter. Both atrial fibrillation and atrial flutter have been reported in open label partial-onset seizure trials and in postmarketing experience. In adult patients with diabetic neuropathy, for which VIMPAT is not indicated, 0.5% of patients treated with VIMPAT experienced an adverse reaction of atrial fibrillation or atrial flutter, compared to 0% of placebo-treated patients. VIMPAT administration may predispose to atrial arrhythmias (atrial fibrillation or flutter), especially in patients with diabetic neuropathy and/or cardiovascular disease.

5.4 Syncope

In the short-term controlled trials of VIMPAT in adult patients with partial-onset seizures with no significant system illnesses, there was no increase in syncope compared to placebo. In the short-term controlled trials in adult patients with diabetic neuropathy, for which VIMPAT is not indicated, 1.2% of patients who were treated with VIMPAT reported an adverse reaction of syncope or loss of consciousness, compared with 0% of placebo-treated patients with diabetic neuropathy. Most of the cases of syncope were observed in patients receiving doses above 400 mg/day. The cause of syncope was not determined in most cases. However, several were associated with either changes in orthostatic blood pressure, atrial flutter/fibrillation (and associated tachycardia), or bradycardia. Cases of syncope have also been observed in open-label clinical partial-onset seizure studies in adult and pediatric patients. These cases were associated with a history of risk factors for cardiac disease and the use of drugs that slow AV conduction.

5.5 Withdrawal of Antiepileptic Drugs (AEDs)

As with all AEDs, VIMPAT should be withdrawn gradually (over a minimum of 1 week) to minimize the potential of increased seizure frequency in patients with seizure disorders.

5.6 Drug Reaction with Eosinophilia and Systemic Symptoms (DRESS)/Multi-Organ Hypersensitivity

Drug Reaction with Eosinophilia and Systemic Symptoms (DRESS), also known as multi-organ hypersensitivity, has been reported in patients taking antiepileptic drugs, including VIMPAT. Some of these events have been fatal or life-threatening. DRESS typically, although not exclusively, presents with fever, rash, lymphadenopathy and/or facial swelling, in association with other organ system involvement, such as hepatitis, nephritis, hematologic abnormalities, myocarditis, or myositis, sometimes resembling an acute viral infection. Eosinophilia is often present. This disorder is variable in its expression, and other organ systems not noted here may be involved. It is important to note that early manifestations of hypersensitivity (e.g., fever, lymphadenopathy) may be present even though rash is not evident. If such signs or symptoms are present, the patient should be evaluated immediately. VIMPAT should be discontinued if an alternative etiology for the signs or symptoms cannot be established.

5.7 Risks in Patients with Phenylketonuria

Phenylalanine can be harmful in patients with phenylketonuria (PKU). VIMPAT oral solution contains aspartame, a source of phenylalanine. A 200 mg dose of VIMPAT oral solution (equivalent to 20 mL) contains 0.32 mg of phenylalanine. Before prescribing VIMPAT oral solution to a patient with PKU, consider the combined daily amount of phenylalanine from all sources, including VIMPAT oral solution.

6 ADVERSE REACTIONS

The following serious adverse reactions are described below and elsewhere in the labeling:

- Suicidal Behavior and Ideation [see Warnings and Precautions (5.1)]
- Dizziness and Ataxia [see Warnings and Precautions (5.2)]
- Cardiac Rhythm and Conduction Abnormalities [see Warnings and Precautions (5.3)]
- Syncope [see Warnings and Precautions (5.4)]
- Drug Reaction with Eosinophilia and Systemic Symptoms (DRESS)/Multiorgan Hypersensitivity Reactions [see Warnings and Precautions (5.6)]

6.1 Clinical Trials Experience

Because clinical trials are conducted under widely varying conditions, adverse reaction rates observed in the clinical trials of a drug cannot be directly compared to rates in the clinical trials of another drug and may not reflect the rates observed in practice.

VIMPAT Tablet and Oral Solution in Adults

In the premarketing development of adjunctive therapy for partial-onset seizures, 1327 adult patients received VIMPAT tablets in controlled and uncontrolled trials, of whom 1000 were treated for longer than 6 months, and 852 for longer than 12 months. The monotherapy development program for partial-onset seizures included 425 adult patients, 310 of whom were treated for longer than 6 months, and 254 for longer than 12 months.

Partial-Onset Seizures

Monotherapy Historical-Control Trial (Study 1)

In the monotherapy trial for partial-onset seizures, 16% of patients randomized to receive VIMPAT at the recommended doses of 300 and 400 mg/day discontinued from the trial as a result of an adverse reaction. The adverse reaction most commonly (≥1% on VIMPAT) leading to discontinuation was dizziness.

Adverse reactions that occurred in this study were generally similar to those that occurred in adjunctive placebo-controlled studies. One adverse reaction, insomnia, occurred at a rate of ≥2% and was not reported at a similar rate in previous studies. This adverse reaction has also been observed in postmarketing experience [see Adverse Reactions (6.2)] . Because this study did not include a placebo control group, causality could not be established.

Dizziness, headache, nausea, somnolence, and fatigue all occurred at lower incidences during the AED Withdrawal Phase and Monotherapy Phase, compared with the Titration Phase [see Clinical Studies (14.1)] .

Adjunctive Therapy Controlled Trials (Studies 2, 3, and 4)

In adjunctive therapy controlled clinical trials for partial-onset seizures, the rate of discontinuation as a result of an adverse reaction was 8% and 17% in patients randomized to receive VIMPAT at the recommended doses of 200 and 400 mg/day, respectively, 29% at 600 mg/day (1.5 times greater than the maximum recommended dose), and 5% in patients randomized to receive placebo. The adverse reactions most commonly (>1% on VIMPAT and greater than placebo) leading to discontinuation were dizziness, ataxia, vomiting, diplopia, nausea, vertigo, and blurred vision.

Table 4 gives the incidence of adverse reactions that occurred in ≥2% of adult patients with partial-onset seizures in the VIMPAT total group and for which the incidence was greater than placebo.

Table 4: Adverse Reactions Incidence in Adjunctive Therapy Pooled, Placebo-Controlled Trials in Adult Patients with Partial-Onset Seizures (Studies 2, 3, and 4)
Adverse Reaction | Placebo N=364 % | VIMPAT 200 mg/day N=270 % | VIMPAT 400 mg/day N=471 % | VIMPAT 600 mg/day [600 mg dose is 1.5 times greater than the maximum recommended dose.] N=203 % | VIMPAT Total N=944 %
Ear and labyrinth disorder
Vertigo | 1 | 5 | 3 | 4 | 4
Eye disorders
Diplopia | 2 | 6 | 10 | 16 | 11
Blurred Vision | 3 | 2 | 9 | 16 | 8
Gastrointestinal disorders
Nausea | 4 | 7 | 11 | 17 | 11
Vomiting | 3 | 6 | 9 | 16 | 9
Diarrhea | 3 | 3 | 5 | 4 | 4
General disorders and administration site conditions
Fatigue | 6 | 7 | 7 | 15 | 9
Gait disturbance | <1 | <1 | 2 | 4 | 2
Asthenia | 1 | 2 | 2 | 4 | 2
Injury, poisoning and procedural complications
Contusion | 3 | 3 | 4 | 2 | 3
Skin laceration | 2 | 2 | 3 | 3 | 3
Nervous system disorders
Dizziness | 8 | 16 | 30 | 53 | 31
Headache | 9 | 11 | 14 | 12 | 13
Ataxia | 2 | 4 | 7 | 15 | 8
Somnolence | 5 | 5 | 8 | 8 | 7
Tremor | 4 | 4 | 6 | 12 | 7
Nystagmus | 4 | 2 | 5 | 10 | 5
Balance disorder | 0 | 1 | 5 | 6 | 4
Memory impairment | 2 | 1 | 2 | 6 | 2
Psychiatric disorders
Depression | 1 | 2 | 2 | 2 | 2
Skin and subcutaneous disorders
Pruritus | 1 | 3 | 2 | 3 | 2

The overall adverse reaction rate was similar in male and female patients. Although there were few non-Caucasian patients, no differences in the incidences of adverse reactions compared to Caucasian patients were observed.

VIMPAT Tablet and Oral Solution in Pediatric Patients

Safety of VIMPAT was evaluated in clinical studies of pediatric patients 1 month to less than 17 years of age for the treatment of partial-onset seizures. Across studies in pediatric patients with partial-onset seizures, 847 patients 1 month to less than 17 years of age received VIMPAT oral solution or tablet, of whom 596 received VIMPAT for at least 1 year. Adverse reactions reported in clinical studies of pediatric patients 1 month to less than 17 years of age were similar to those seen in adult patients.

Primary Generalized Tonic-Clonic Seizures in Patients (4 Years of Age and Older) Adjunctive Therapy Trial (Study 5)

In the adjunctive therapy placebo-controlled trial for primary generalized tonic-clonic seizures, adverse reactions that occurred in the study were generally similar to those that occurred in partial-onset seizure placebo-controlled studies. The most common adverse reactions (≥ 10% on VIMPAT) reported in patients treated with VIMPAT were dizziness (23%), somnolence (17%), headache (14%), and nausea (10%), compared to 7%, 14%, 10%, and 6%, respectively, of patients who received placebo. Additionally, an adverse reaction not previously reported of myoclonic epilepsy was reported in 3% of patients treated with VIMPAT compared to 1% of patients who received placebo. It is also noted that 2 patients receiving VIMPAT had acute worsening of seizures shortly after drug initiation, including one episode of status epilepticus, compared to no patients receiving placebo.

Laboratory Abnormalities

Abnormalities in liver function tests have occurred in controlled trials with VIMPAT in adult patients with partial-onset seizures who were taking 1 to 3 concomitant anti-epileptic drugs. Elevations of ALT to ≥3× ULN occurred in 0.7% (7/935) of VIMPAT patients and 0% (0/356) of placebo patients. One case of hepatitis with transaminases >20× ULN occurred in one healthy subject 10 days after VIMPAT treatment completion, along with nephritis (proteinuria and urine casts). Serologic studies were negative for viral hepatitis. Transaminases returned to normal within one month without specific treatment. At the time of this event, bilirubin was normal. The hepatitis/nephritis was interpreted as a delayed hypersensitivity reaction to VIMPAT.

Other Adverse Reactions

The following is a list of adverse reactions reported by patients treated with VIMPAT in all clinical trials in adult patients, including controlled trials and long-term open-label extension trials. Adverse reactions addressed in other tables or sections are not listed here.

Blood and lymphatic system disorders: neutropenia, anemia

Cardiac disorders: palpitations

Ear and labyrinth disorders: tinnitus

Gastrointestinal disorders: constipation, dyspepsia, dry mouth, oral hypoaesthesia

General disorders and administration site conditions: irritability, pyrexia, feeling drunk

Injury, poisoning, and procedural complications: fall

Musculoskeletal and connective tissue disorders: muscle spasms

Nervous system disorders: paresthesia, cognitive disorder, hypoaesthesia, dysarthria, disturbance in attention, cerebellar syndrome

Psychiatric disorders: confusional state, mood altered, depressed mood

VIMPAT Injection

Adult Patients (17 Years and Older)

Adverse reactions with intravenous administration to adult patients with partial-onset seizures generally were similar to those that occurred with the oral formulation, although intravenous administration was associated with local adverse reactions such as injection site pain or discomfort (2.5%), irritation (1%), and erythema (0.5%). One case of profound bradycardia (26 bpm: BP 100/60 mmHg) occurred in a patient during a 15-minute infusion of 150 mg VIMPAT. This patient was on a beta-blocker. Infusion was discontinued and the patient experienced a rapid recovery.

The safety of a 15-minute loading dose administration of VIMPAT Injection 200 mg to 400 mg followed by oral administration of VIMPAT given twice daily at the same total daily dose as the initial intravenous infusion was assessed in an open-label study in adult patients with partial-onset seizures. Patients had to have been maintained on a stable dose regimen of 1 to 2 marketed antiepileptics for at least 28 days prior to treatment assignment. Treatment groups were as follows:

- Single dose of intravenous VIMPAT Injection 200 mg followed by oral VIMPAT 200 mg/day (100 mg every 12 hours)
- Single dose of intravenous VIMPAT Injection 300 mg followed by oral VIMPAT 300 mg/day (150 mg every 12 hours)
- Single dose of intravenous VIMPAT Injection 400 mg followed by oral VIMPAT 400 mg/day (200 mg every 12 hours).

Table 5 gives the incidence of adverse reactions that occurred in ≥5% of adult patients in any VIMPAT dosing group.

Table 5: Adverse Reactions in a 15-minute Infusion Study in Adult Patients with Partial-Onset Seizures
Adverse Reaction | VIMPAT 200 mg N=25 % | VIMPAT 300 mg N=50 % | VIMPAT 400 mg N=25 % | VIMPAT Total N=100 %
Eye disorders
Diplopia | 4 | 6 | 20 | 9
Blurred Vision | 0 | 4 | 12 | 5
Gastrointestinal disorders
Nausea | 0 | 16 | 24 | 14
Dry mouth | 0 | 6 | 12 | 6
Vomiting | 0 | 4 | 12 | 5
Oral Paresthesia | 4 | 4 | 8 | 5
Oral Hypoesthesia | 0 | 6 | 8 | 5
Diarrhea | 0 | 8 | 0 | 4
General disorders/administration site conditions
Fatigue | 0 | 18 | 12 | 12
Gait disturbance | 8 | 2 | 0 | 3
Chest pain | 0 | 0 | 12 | 3
Nervous system disorders
Dizziness | 20 | 46 | 60 | 43
Somnolence | 0 | 34 | 36 | 26
Headache | 8 | 4 | 16 | 8
Paresthesia | 8 | 6 | 4 | 6
Tremor | 0 | 6 | 4 | 4
Abnormal Coordination | 0 | 6 | 0 | 3
Skin & subcutaneous tissue disorders
Pruritus | 0 | 6 | 4 | 4
Hyperhidrosis | 0 | 0 | 8 | 2

Adverse reactions that occurred with infusion of VIMPAT 200 mg over 15-minutes followed by VIMPAT 100 mg administered orally twice per day were similar in frequency to those that occurred in 3-month adjunctive therapy controlled trials. Considering the difference in period of observations (1 week vs. 3 months), the incidence of CNS adverse reactions, such as dizziness, somnolence, and paresthesia may be higher with 15-minute administration of VIMPAT Injection than with administration over a 30-to 60-minute period.

The adverse reactions associated with VIMPAT injection in adult patients with primary generalized tonic-clonic seizures are expected to be similar to those seen in adults with partial-onset seizures.

Pediatric Patients (1 Month to less than 17 Years of Age)

The safety of VIMPAT injection was evaluated in a multicenter, open-label study of 103 pediatric patients 1 month to less than 17 years of age with epilepsy. Infusions were primarily administered over a 30 to 60 minute time period; infusion times less than 30 minutes were not adequately studied in pediatric patients [see Dosage and Administration (2.7)] . Although no serious or severe adverse reactions were noted at the time of infusion in this small study, the adverse reactions associated with VIMPAT injection in pediatric patients are expected to be similar to those noted in adults.

In a retrospective cohort study of electronic healthcare records of 686 pediatric patients who started VIMPAT with intravenous dosing, the incidence of rash within 30 days of discontinuation of intravenous VIMPAT was two-fold higher in the cohort of patients who were initiated with the alternate initial dosing regimen to achieve the maintenance dosage in a shorter timeframe [see Dosage and Administration (2.2)] compared to the cohort of patients who were initiated with a lower initial dosage regimen [see Dosage and Administration (2.1)] .

6.2 Postmarketing Experience

The following adverse reactions have been identified during post-approval use of VIMPAT. Because these reactions are reported voluntarily from a population of uncertain size, it is not always possible to reliably estimate their frequency or establish a causal relationship to drug exposure.

Blood and lymphatic system disorders: Agranulocytosis
Psychiatric disorders: Aggression, agitation, hallucination, insomnia, psychotic disorder
Skin and subcutaneous tissue disorders: Angioedema, rash, urticaria, Stevens-Johnson syndrome, toxic epidermal necrolysis.
Neurologic disorders: Dyskinesia, new or worsening seizures

7 DRUG INTERACTIONS

7.1 Strong CYP3A4 or CYP2C9 Inhibitors

Patients with renal or hepatic impairment who are taking strong inhibitors of CYP3A4 and CYP2C9 may have a significant increase in exposure to VIMPAT. Dose reduction may be necessary in these patients.

7.2 Concomitant Medications that Affect Cardiac Conduction

VIMPAT should be used with caution in patients on concomitant medications that affect cardiac conduction (sodium channel blockers, beta-blockers, calcium channel blockers, potassium channel blockers) including those that prolong PR interval (including sodium channel blocking AEDs), because of a risk of AV block, bradycardia, or ventricular tachyarrhythmia. In such patients, obtaining an ECG before beginning VIMPAT, and after VIMPAT is titrated to steady-state, is recommended. In addition, these patients should be closely monitored if they are administered VIMPAT through the intravenous route [see Warnings and Precautions (5.3)] .

8 USE IN SPECIFIC POPULATIONS

8.1 Pregnancy

Pregnancy Exposure Registry

There is a pregnancy exposure registry that monitors pregnancy outcomes in women exposed to antiepileptic drugs (AEDs), such as VIMPAT, during pregnancy. Encourage women who are taking VIMPAT during pregnancy to enroll in the North American Antiepileptic Drug (NAAED) pregnancy registry by calling 1-888-233-2334 or visiting http://www.aedpregnancyregistry.org/.

Risk Summary

Available data from the North American Antiepileptic Drug (NAAED) pregnancy registry, a prospective cohort study, case reports, and a case series with VIMPAT use in pregnant women are insufficient to identify a drug-associated risk of major birth defects, miscarriage or other adverse maternal or fetal outcomes .Lacosamide produced developmental toxicity (increased embryofetal and perinatal mortality, growth deficit) in rats following administration during pregnancy. Developmental neurotoxicity was observed in rats following administration during a period of postnatal development corresponding to the third trimester of human pregnancy. These effects were observed at doses associated with clinically relevant plasma exposures (see Data) .

The background risk of major birth defects and miscarriage for the indicated population is unknown. All pregnancies have a background risk of birth defect, loss, or other adverse outcomes. In the U.S. general population the estimated background risk of major birth defects and miscarriage in clinically recognized pregnancies is 2-4% and 15-20%, respectively.

Data

Animal Data

Oral administration of lacosamide to pregnant rats (20, 75, or 200 mg/kg/day) and rabbits (6.25, 12.5, or 25 mg/kg/day) during the period of organogenesis did not produce any effects on the incidences of fetal structural abnormalities. However, the maximum doses evaluated were limited by maternal toxicity in both species and embryofetal death in rats. These doses were associated with maternal plasma lacosamide exposures (AUC) approximately 2 and 1 times (rat and rabbit, respectively) that in humans at the maximum recommended human dose (MRHD) of 400 mg/day.

In two studies in which lacosamide (25, 70, or 200 mg/kg/day and 50, 100, or 200 mg/kg/day) was orally administered to rats throughout pregnancy and lactation, increased perinatal mortality and decreased body weights in the offspring were observed at the highest dose tested. The no-effect dose for pre- and postnatal developmental toxicity in rats (70 mg/kg/day) was associated with a maternal plasma lacosamide AUC similar to that in humans at the MRHD.

Oral administration of lacosamide (30, 90, or 180 mg/kg/day) to rats during the neonatal and juvenile periods of development resulted in decreased brain weights and long-term neurobehavioral changes (altered open field performance, deficits in learning and memory). The early postnatal period in rats is generally thought to correspond to late pregnancy in humans in terms of brain development. The no-effect dose for developmental neurotoxicity in rats was associated with a plasma lacosamide AUC less than that in humans at the MRHD.

In Vitro Data

Lacosamide has been shown in vitroto interfere with the activity of collapsin response mediator protein-2 (CRMP-2), a protein involved in neuronal differentiation and control of axonal outgrowth. Potential adverse effects on CNS development related to this activity cannot be ruled out.

8.2 Lactation

Risk Summary

Data from published literature indicate that lacosamide is present in human milk. There are reports of increased sleepiness in breastfed infants exposed to lacosamide (see Clinical Considerations). There is no information on the effects of lacosamide on milk production.

The developmental and health benefits of breastfeeding should be considered along with the mother's clinical need for VIMPAT and any potential adverse effects on the breastfed infant from VIMPAT or from the underlying maternal condition.

Clinical Considerations

Monitor infants exposed to VIMPAT through breastmilk for excess sedation.

8.4 Pediatric Use

Partial-Onset Seizures

Safety and effectiveness of VIMPAT for the treatment of partial-onset seizures have been established in pediatric patients 1 month to less than 17 years of age. Use of VIMPAT in this age group is supported by evidence from adequate and well-controlled studies of VIMPAT in adults with partial-onset seizures, pharmacokinetic data from adult and pediatric patients, and safety data in 847 pediatric patients 1 month to less than 17 years of age [see Adverse Reactions (6.1), Clinical Pharmacology (12.3), and Clinical Studies (14.1, 14.2)] .

Safety and effectiveness in pediatric patients below 1 month of age have not been established.

Primary Generalized Tonic-Clonic Seizures

Safety and effectiveness of VIMPAT as adjunctive therapy in the treatment of primary generalized tonic-clonic seizures in pediatric patients with idiopathic generalized epilepsy 4 years of age and older was established in a 24-week double-blind, randomized, placebo-controlled, parallel-group, multi-center study (Study 5), which included 37 pediatric patients 4 years to less than 17 years of age [see Adverse Reactions (6.1)and Clinical Studies (14.3)] .

Safety and effectiveness in pediatric patients below the age of 4 years have not been established.

Animal Data

Lacosamide has been shown in vitroto interfere with the activity of collapsin response mediator protein-2 (CRMP-2), a protein involved in neuronal differentiation and control of axonal outgrowth. Potential related adverse effects on CNS development cannot be ruled out. Administration of lacosamide to rats during the neonatal and juvenile periods of postnatal development (approximately equivalent to neonatal through adolescent development in humans) resulted in decreased brain weights and long-term neurobehavioral changes (altered open field performance, deficits in learning and memory). The no-effect dose for developmental neurotoxicity in rats was associated with a plasma lacosamide exposure (AUC) less than that in humans at the maximum recommended human dose of 400 mg/day.

8.5 Geriatric Use

There were insufficient numbers of elderly patients enrolled in partial-onset seizure trials (n=18) to adequately determine whether they respond differently from younger patients.

No VIMPAT dose adjustment based on age is necessary. In elderly patients, dose titration should be performed with caution, usually starting at the lower end of the dosing range, reflecting the greater frequency of decreased hepatic function, decreased renal function, increased cardiac conduction abnormalities, and polypharmacy [see Dosage and Administration (2.1, 2.4, 2.5)and Clinical Pharmacology (12.3)] .

8.6 Renal Impairment

No dose adjustment is necessary in patients with mild to moderate renal impairment (CLCR≥30 mL/min). In patients with severe renal impairment (CLCR<30 mL/min as estimated by the Cockcroft-Gault equation for adults; CLCR<30 mL/min/1.73m^2as estimated by the Schwartz equation for pediatric patients) and in those with end-stage renal disease, a reduction of 25% of the maximum dosage is recommended [see Dosage and Administration (2.4)and Clinical Pharmacology (12.3)] .

In all patients with renal impairment, dose initiation and titration should be based on clinical response and tolerability.

VIMPAT is effectively removed from plasma by hemodialysis. Dosage supplementation of up to 50% following hemodialysis should be considered.

8.7 Hepatic Impairment

For adult and pediatric patients with mild to moderate hepatic impairment, a reduction of 25% of the maximum dosage is recommended. Patients with mild to moderate hepatic impairment should be observed closely for adverse reactions, and dose initiation and titration should be based on clinical response and tolerability [see Dosage and Administration (2.5), Clinical Pharmacology (12.3)] .

The pharmacokinetics of lacosamide has not been evaluated in severe hepatic impairment. VIMPAT use is not recommended in patients with severe hepatic impairment.

9 DRUG ABUSE AND DEPENDENCE

9.1 Controlled Substance

VIMPAT contains lacosamide, a Schedule V controlled substance.

9.2 Abuse

Abuse is the intentional, non-therapeutic use of a drug, even once, for its desirable psychological or physiological effects. In a human abuse potential study, single doses of 200 mg (equal to the maximum single dosage) and 800 mg lacosamide (equal to twice the recommended daily maintenance dosage) produced euphoria-type subjective responses that differentiated statistically from placebo; at 800 mg, these euphoria-type responses were statistically indistinguishable from those produced by alprazolam, a Schedule IV drug. The duration of the euphoria-type responses following lacosamide was less than that following alprazolam. A high rate of euphoria was also reported as an adverse event in the human abuse potential study following single doses of 800 mg lacosamide (15% [5/34]) compared to placebo (0%) and in two pharmacokinetic studies following single and multiple doses of 300-800 mg lacosamide (ranging from 6% [2/33] to 25% [3/12]) compared to placebo (0%). However, the rate of euphoria reported as an adverse event in the VIMPAT development program at therapeutic doses was less than 1%.

9.3 Dependence

Physical dependence is a state that develops as a result of physiological adaptation in response to repeated drug use, manifested by withdrawal signs and symptoms after abrupt discontinuation or a significant dose reduction of a drug. Abrupt termination of lacosamide in clinical trials with diabetic neuropathic pain patients produced no signs or symptoms that are associated with a withdrawal syndrome indicative of physical dependence. However, psychological dependence cannot be excluded due to the ability of lacosamide to produce euphoria-type adverse events in humans.

10 OVERDOSAGE

Events reported after an intake of more than 800 mg (twice the maximum recommended daily dosage) of VIMPAT include dizziness, nausea, and seizures (generalized tonic-clonic seizures, status epilepticus). Cardiac conduction disorders, confusion, decreased level of consciousness, cardiogenic shock, cardiac arrest, and coma have also been observed. Fatalities have occurred following lacosamide overdoses of several grams.

There is no specific antidote for overdose with VIMPAT. Standard decontamination procedures should be followed. General supportive care of the patient is indicated including monitoring of vital signs and observation of the clinical status of patient. A Certified Poison Control Center should be contacted for up to date information on the management of overdose with VIMPAT.

Standard hemodialysis procedures result in significant clearance of VIMPAT (reduction of systemic exposure by 50% in 4 hours). Hemodialysis may be indicated based on the patient's clinical state or in patients with significant renal impairment.

11 DESCRIPTION

The chemical name of lacosamide, the single (R)-enantiomer, is (R)-2-acetamido-N-benzyl-3-methoxypropionamide (IUPAC). Lacosamide is a functionalized amino acid. Its molecular formula is C13H18N2O3and its molecular weight is 250.30. The chemical structure is:

Lacosamide is a white to light yellow powder. It is sparingly soluble in water and slightly soluble in acetonitrile and ethanol.

11.1 VIMPAT Tablets

VIMPAT tablets for oral administration contain lacosamide and the following inactive ingredients: colloidal silicon dioxide, crospovidone, hydroxypropylcellulose, magnesium stearate, microcrystalline cellulose, polyethylene glycol, polyvinyl alcohol, talc, titanium dioxide, and dye pigments as specified below:

VIMPAT tablets are supplied as debossed tablets and contain the following coloring agents:

50 mg tablets: red iron oxide, black iron oxide, FD&C Blue #2/indigo carmine aluminum lake

100 mg tablets: yellow iron oxide

150 mg tablets: yellow iron oxide, red iron oxide, black iron oxide

200 mg tablets: FD&C Blue #2/indigo carmine aluminum lake

11.2 VIMPAT Injection

VIMPAT injection is a clear, colorless, sterile solution containing 10 mg lacosamide per mL for intravenous infusion. One 20-mL vial contains 200 mg of lacosamide drug substance. The inactive ingredients are sodium chloride (7.62 mg/mL) and water for injection. Hydrochloric acid is used for pH adjustment. VIMPAT injection has a pH of 3.8 to 5.0.

11.3 VIMPAT Oral Solution

VIMPAT oral solution contains 10 mg of lacosamide per mL. The inactive ingredients are purified water, sorbitol solution, glycerin, polyethylene glycol, carboxymethylcellulose sodium, acesulfame potassium, methylparaben, flavoring (including natural and artificial flavors, propylene glycol, aspartame, and maltol), anhydrous citric acid and sodium chloride.

12 CLINICAL PHARMACOLOGY

12.1 Mechanism of Action

The precise mechanism by which VIMPAT exerts its antiepileptic effects in humans remains to be fully elucidated. In vitroelectrophysiological studies have shown that lacosamide selectively enhances slow inactivation of voltage-gated sodium channels, resulting in stabilization of hyperexcitable neuronal membranes and inhibition of repetitive neuronal firing.

12.2 Pharmacodynamics

A pharmacokinetic-pharmacodynamic (efficacy) analysis was performed based on the pooled data from the 3 efficacy trials for partial-onset seizures. Lacosamide exposure is correlated with the reduction in seizure frequency. However, doses above 400 mg/day do not appear to confer additional benefit in group analyses.

Cardiac Electrophysiology

Electrocardiographic effects of VIMPAT were determined in a double-blind, randomized clinical pharmacology trial of 247 healthy subjects. Chronic oral doses of 400 and 800 mg/day (equal to and two times the maximum daily recommended dose, respectively) were compared with placebo and a positive control (400 mg moxifloxacin). VIMPAT did not prolong QTc interval and did not have a dose-related or clinically important effect on QRS duration. VIMPAT produced a small, dose-related increase in mean PR interval. At steady-state, the time of the maximum observed mean PR interval corresponded with tmax. The placebo-subtracted maximum increase in PR interval (at tmax) was 7.3 ms for the 400 mg/day group and 11.9 ms for the 800 mg/day group. For patients who participated in the controlled trials, the placebo-subtracted mean maximum increase in PR interval for a 400 mg/day VIMPAT dose was 3.1 ms in patients with partial-onset seizures and 9.4 ms for patients with diabetic neuropathy.

12.3 Pharmacokinetics

The pharmacokinetics of VIMPAT have been studied in healthy adult subjects (age range 18 to 87), adults with partial-onset seizures, adults with diabetic neuropathy, and subjects with renal and hepatic impairment.

The pharmacokinetics of VIMPAT are similar in healthy subjects, patients with partial-onset seizures, and patients with primary generalized tonic-clonic seizures.

VIMPAT is completely absorbed after oral administration with negligible first-pass effect with a high absolute bioavailability of approximately 100%. The maximum lacosamide plasma concentrations occur approximately 1-to-4-hour post-dose after oral dosing, and elimination half-life is approximately 13 hours. Steady state plasma concentrations are achieved after 3 days of twice daily repeated administration. Pharmacokinetics of VIMPAT are dose proportional (100-800 mg) and time invariant, with low inter- and intra-subject variability. Compared to lacosamide the major metabolite, O-desmethyl metabolite, has a longer Tmax(0.5 to 12 hours) and elimination half-life (15-23 hours).

Absorption and Bioavailability

VIMPAT is completely absorbed after oral administration. The oral bioavailability of VIMPAT tablets is approximately 100%. Food does not affect the rate and extent of absorption.

After intravenous administration, Cmaxis reached at the end of infusion. The 30- and 60-minute intravenous infusions are bioequivalent to the oral tablet. For the 15-minute intravenous infusion, bioequivalence was met for AUC(0-tz)but not for Cmax. The point estimate of Cmaxwas 20% higher than Cmaxfor oral tablet and the 90% CI for Cmaxexceeded the upper boundary of the bioequivalence range.

In a trial comparing the oral tablet with an oral solution containing 10 mg/mL lacosamide, bioequivalence between both formulations was shown.

A single loading dose of 200 mg approximates steady-state concentrations comparable to the 100 mg twice daily oral administration.

Distribution

The volume of distribution is approximately 0.6 L/kg and thus close to the volume of total body water. VIMPAT is less than 15% bound to plasma proteins.

Metabolism and Elimination

VIMPAT is primarily eliminated from the systemic circulation by renal excretion and biotransformation.

After oral and intravenous administration of 100 mg [14C]-lacosamide approximately 95% of radioactivity administered was recovered in the urine and less than 0.5% in the feces. The major compounds excreted were unchanged lacosamide (approximately 40% of the dose), its O-desmethyl metabolite (approximately 30%), and a structurally unknown polar fraction (~20%). The plasma exposure of the major human metabolite, O-desmethyl-lacosamide, is approximately 10% of that of lacosamide. This metabolite has no known pharmacological activity.

The CYP isoforms mainly responsible for the formation of the major metabolite (O-desmethyl) are CYP3A4, CYP2C9, and CYP2C19. The elimination half-life of the unchanged drug is approximately 13 hours and is not altered by different doses, multiple dosing or intravenous administration.

There is no enantiomeric interconversion of lacosamide.

Specific Populations

Renal Impairment

Lacosamide and its major metabolite are eliminated from the systemic circulation primarily by renal excretion.

The AUC of VIMPAT was increased approximately 25% in mildly (CLCR50-80 mL/min) and moderately (CLCR30-50 mL/min) and 60% in severely (CLCR≤30 mL/min) renally impaired patients compared to subjects with normal renal function (CLCR>80 mL/min), whereas Cmaxwas unaffected. VIMPAT is effectively removed from plasma by hemodialysis. Following a 4-hour hemodialysis treatment, AUC of VIMPAT is reduced by approximately 50% [see Dosage and Administration (2.4)] .

Hepatic Impairment

Lacosamide undergoes metabolism. Subjects with moderate hepatic impairment (Child-Pugh B) showed higher plasma concentrations of lacosamide (approximately 50-60% higher AUC compared to healthy subjects). The pharmacokinetics of lacosamide have not been evaluated in severe hepatic impairment [see Dosage and Administration (2.5)] .

Pediatric Patients (1 month to less than 17 Years of Age)

A multicenter, double-blind, randomized, placebo-controlled, parallel-group study with a 20-day titration period and 7-day maintenance period using VIMPAT oral solution (8mg/kg/day to 12mg/kg/day) was conducted in 255 (128 were randomized to VIMPAT and 127 were randomized to placebo) pediatric patients with epilepsy 1 month to less than 4 years of age with uncontrolled partial-onset seizures. The pediatric pharmacokinetic profile of VIMPAT was determined in a population pharmacokinetic analysis using sparse plasma concentration data obtained in six placebo-controlled studies and five open-label studies in 1655 adult and pediatric patients with epilepsy aged 1 month to less than 17 years who received intravenous, oral solution, or oral tablet formulations.

A weight based dosing regimen is necessary to achieve lacosamide exposures in pediatric patients 1 month to less than 17 years of age similar to those observed in adults treated at effective doses of VIMPAT [see Dosage and Administration (2.1)]. For patients weighing 10 kg, 28.9 kg (the mean population body weight), and 70 kg, the typical plasma half-life (t1/2) is 7.2 hours, 10.6 hours, and 14.8 hours, respectively. Steady state plasma concentrations are achieved after 3 days of twice daily repeated administration.

The pharmacokinetics of VIMPAT in pediatric patients are similar when used as monotherapy or as adjunctive therapy for the treatment of partial-onset seizures and as adjunctive therapy for the treatment of primary generalized tonic-clonic seizures.

Geriatric Patients

In the elderly (>65 years), dose and body-weight normalized AUC and Cmaxis about 20% increased compared to young subjects (18-64 years). This may be related to body weight and decreased renal function in elderly subjects.

Gender

VIMPAT clinical trials indicate that gender does not have a clinically relevant influence on the pharmacokinetics of VIMPAT.

Race

There are no clinically relevant differences in the pharmacokinetics of VIMPAT between Asian, Black, and Caucasian subjects.

CYP2C19 Polymorphism

There are no clinically relevant differences in the pharmacokinetics of VIMPAT between CYP2C19 poor metabolizers and extensive metabolizers. Results from a trial in poor metabolizers (PM) (N=4) and extensive metabolizers (EM) (N=8) of cytochrome P450 (CYP) 2C19 showed that lacosamide plasma concentrations were similar in PMs and EMs, but plasma concentrations and the amount excreted into urine of the O-desmethyl metabolite were about 70% reduced in PMs compared to EMs.

Drug Interactions

In Vitro Assessment of Drug Interactions

In vitrometabolism studies indicate that lacosamide does not induce the enzyme activity of drug metabolizing cytochrome P450 isoforms CYP1A2, 2B6, 2C9, 2C19 and 3A4. Lacosamide did not inhibit CYP 1A1, 1A2, 2A6, 2B6, 2C8, 2C9, 2D6, 2E1, 3A4/5 at plasma concentrations observed in clinical studies.

In vitrodata suggest that lacosamide has the potential to inhibit CYP2C19 at therapeutic concentrations. However, an in vivostudy with omeprazole did not show an inhibitory effect on omeprazole pharmacokinetics.

Lacosamide was not a substrate or inhibitor for P-glycoprotein.

Lacosamide is a substrate of CYP3A4, CYP2C9, and CYP2C19. Patients with renal or hepatic impairment who are taking strong inhibitors of CYP3A4 and CYP2C9 may have increased exposure to lacosamide.

Since <15% of lacosamide is bound to plasma proteins, a clinically relevant interaction with other drugs through competition for protein binding sites is unlikely.

In Vivo Assessment of Drug Interactions

- Drug interaction studies with AEDs
  - Effect of VIMPAT on concomitant AEDs
    VIMPAT 400 mg/day had no influence on the pharmacokinetics of 600 mg/day valproic acid and 400 mg/day carbamazepine in healthy subjects.
    The placebo-controlled clinical studies in patients with partial-onset seizures showed that steady-state plasma concentrations of levetiracetam, carbamazepine, carbamazepine epoxide, lamotrigine, topiramate, oxcarbazepine monohydroxy derivative (MHD), phenytoin, valproic acid, phenobarbital, gabapentin, clonazepam, and zonisamide were not affected by concomitant intake of VIMPAT at any dose.
  - Effect of concomitant AEDs on VIMPAT
    Drug-drug interaction studies in healthy subjects showed that 600 mg/day valproic acid had no influence on the pharmacokinetics of 400 mg/day VIMPAT. Likewise, 400 mg/day carbamazepine had no influence on the pharmacokinetics of VIMPAT in a healthy subject study. Population pharmacokinetics results in patients with partial-onset seizures showed small reductions (15% to 20% lower) in lacosamide plasma concentrations when VIMPAT was coadministered with carbamazepine, phenobarbital or phenytoin.
- Drug-drug interaction studies with other drugs
  - Digoxin
    There was no effect of VIMPAT (400 mg/day) on the pharmacokinetics of digoxin (0.5 mg once daily) in a study in healthy subjects.
  - Metformin
    There were no clinically relevant changes in metformin levels following coadministration of VIMPAT (400 mg/day).
    Metformin (500 mg three times a day) had no effect on the pharmacokinetics of VIMPAT (400 mg/day).
  - Omeprazole
    Omeprazole is a CYP2C19 substrate and inhibitor.
    There was no effect of VIMPAT (600 mg/day) on the pharmacokinetics of omeprazole (40 mg single dose) in healthy subjects. The data indicated that lacosamide had little in vivoinhibitory or inducing effect on CYP2C19.
    Omeprazole at a dose of 40 mg once daily had no effect on the pharmacokinetics of VIMPAT (300 mg single dose). However, plasma levels of the O-desmethyl metabolite were reduced about 60% in the presence of omeprazole.
  - Midazolam
    Midazolam is a 3A4 substrate.
    There was no effect of VIMPAT (200 mg single dose or repeat doses of 400 mg/day given as 200 mg BID) on the pharmacokinetics of midazolam (single dose, 7.5 mg), indicating no inhibitory or inducing effects on CYP3A4.
  - Oral Contraceptives
    There was no influence of VIMPAT (400 mg/day) on the pharmacodynamics and pharmacokinetics of an oral contraceptive containing 0.03 mg ethinylestradiol and 0.15 mg levonorgestrel in healthy subjects, except that a 20% increase in ethinylestradiol Cmaxwas observed.
  - Warfarin
    Co-administration of VIMPAT (400 mg/day) with warfarin (25 mg single dose) did not result in a clinically relevant change in the pharmacokinetic and pharmacodynamic effects of warfarin in a study in healthy male subjects.

13 NONCLINICAL TOXICOLOGY

13.1 Carcinogenesis, Mutagenesis, Impairment of Fertility

Carcinogenesis

There was no evidence of drug related carcinogenicity in mice or rats. Mice and rats received lacosamide once daily by oral administration for 104 weeks at doses producing plasma exposures (AUC) up to approximately 1 and 3 times, respectively, the plasma AUC in humans at the maximum recommended human dose (MRHD) of 400 mg/day.

Mutagenesis

Lacosamide was negative in an in vitroAmes test and an in vivomouse micronucleus assay. Lacosamide induced a positive response in the in vitromouse lymphoma assay.

Fertility

No adverse effects on male or female fertility or reproduction were observed in rats at doses producing plasma exposures (AUC) up to approximately 2 times the plasma AUC in humans at the MRHD.

14 CLINICAL STUDIES

14.1 Monotherapy in Patients with Partial-Onset Seizures

The efficacy of VIMPAT in monotherapy was established in a historical-control, multicenter, randomized trial that included 425 patients, age 16 to 70 years, with partial-onset seizures (Study 1). To be included in Study 1, patients were required to be taking stable doses of 1 or 2 marketed antiepileptic drugs. This treatment continued into the 8 week baseline period. To remain in the study, patients were required to have at least 2 partial-onset seizures per 28 days during the 8 week baseline period. The baseline period was followed by a 3 week titration period, during which VIMPAT was added to the ongoing antiepileptic regimen. This was followed by a 16-week maintenance period (i.e., a 6-week withdrawal period for background antiepileptic drugs, followed by a 10-week monotherapy period). Patients were randomized 3 to 1 to receive VIMPAT 400 mg/day or VIMPAT 300 mg/day. Treatment assignments were blinded. Response to treatment was based upon a comparison of the number of patients who met exit criteria during the maintenance phase, compared to historical controls. The historical control consisted of a pooled analysis of the control groups from 8 studies of similar design, which utilized a sub-therapeutic dose of an antiepileptic drug. Statistical superiority to the historical control was considered to be demonstrated if the upper limit from a 2-sided 95% confidence interval for the percentage of patients meeting exit criteria in patients receiving VIMPAT remained below the lower 95% prediction limit of 65% derived from the historical control data.

The exit criteria were one or more of the following: (1) doubling of average monthly seizure frequency during any 28 consecutive days, (2) doubling of highest consecutive 2-day seizure frequency, (3) occurrence of a single generalized tonic-clonic seizure, (4) clinically significant prolongation or worsening of overall seizure duration, frequency, type or pattern considered by the investigator to require trial discontinuation, (5) status epilepticus or new onset of serial/cluster seizures. The study population profile appeared comparable to that of the historical control population.

For the VIMPAT 400 mg/day group, the estimate of the percentage of patients meeting at least 1 exit criterion was 30% (95% CI: 25%, 36%). The upper limit of the 2-sided 95% CI (36%) was below the threshold of 65% derived from the historical control data, meeting the pre-specified criteria for efficacy. VIMPAT 300 mg/day also met the pre-specified criteria for efficacy.

14.2 Adjunctive Therapy in Patients with Partial-Onset Seizures

The efficacy of VIMPAT as adjunctive therapy in partial-onset seizures was established in three 12-week, randomized, double-blind, placebo-controlled, multicenter trials in adult patients (Study 2, Study 3, and Study 4). Enrolled patients had partial-onset seizures with or without secondary generalization, and were not adequately controlled with 1 to 3 concomitant AEDs. During an 8-week baseline period, patients were required to have an average of ≥4 partial-onset seizures per 28 days with no seizure-free period exceeding 21 days. In these 3 trials, patients had a mean duration of epilepsy of 24 years and a median baseline seizure frequency ranging from 10 to 17 per 28 days. 84% of patients were taking 2 to 3 concomitant AEDs with or without concurrent vagal nerve stimulation.

Study 2 compared doses of VIMPAT 200, 400, and 600 mg/day with placebo. Study 3 compared doses of VIMPAT 400 and 600 mg/day with placebo. Study 4 compared doses of VIMPAT 200 and 400 mg/day with placebo. In all three trials, following an 8-week baseline phase to establish baseline seizure frequency prior to randomization, patients were randomized and titrated to the randomized dose (a 1-step back-titration of VIMPAT 100 mg/day or placebo was allowed in the case of intolerable adverse reactions at the end of the titration phase). During the titration phase, in all 3 adjunctive therapy trials, treatment was initiated at 100 mg/day (50 mg twice daily), and increased in weekly increments of 100 mg/day to the target dose. The titration phase lasted 6 weeks in Study 2 and Study 3, and 4 weeks in Study 4. In all three trials, the titration phase was followed by a maintenance phase that lasted 12 weeks, during which patients were to remain on a stable dose of VIMPAT.

A reduction in 28-day seizure frequency (baseline to maintenance phase), as compared to the placebo group, was the primary variable in all three adjunctive therapy trials. A statistically significant effect was observed with VIMPAT treatment (Figure 1) at doses of 200 mg/day (Study 4), 400 mg/day (Studies 2, 3, and 4), and 600 mg/day (Studies 2 and 3).

Subset evaluations of VIMPAT demonstrate no important differences in seizure control as a function of gender or race, although data on race was limited (about 10% of patients were non-Caucasian).

Figure 2 presents the percentage of patients (X-axis) with a percent reduction in partial seizure frequency (responder rate) from baseline to the maintenance phase at least as great as that represented on the Y-axis. A positive value on the Y-axis indicates an improvement from baseline (i.e., a decrease in seizure frequency), while a negative value indicates a worsening from baseline (i.e., an increase in seizure frequency). Thus, in a display of this type, a curve for an effective treatment is shifted to the left of the curve for placebo. The proportion of patients achieving any particular level of reduction in seizure frequency was consistently higher for the VIMPAT groups, compared to the placebo group. For example, 40% of patients randomized to VIMPAT (400 mg/day) experienced a 50% or greater reduction in seizure frequency, compared to 23% of patients randomized to placebo. Patients with an increase in seizure frequency >100% are represented on the Y-axis as equal to or greater than -100%.

14.3 Adjunctive Therapy in Patients with Primary Generalized Tonic-Clonic Seizures

The efficacy of VIMPAT as adjunctive therapy in patients 4 years of age and older with idiopathic generalized epilepsy experiencing primary generalized tonic-clonic (PGTC) seizures was established in a 24-week double-blind, randomized, placebo-controlled, parallel-group, multi-center study (Study 5). The study consisted of a 12-week historical baseline period, a 4-week prospective baseline period, and a 24-week treatment period (which included a 6-week titration period and an 18-week maintenance period). Eligible patients on a stable dose of 1 to 3 antiepileptic drugs experiencing at least 3 documented PGTC seizures during the 16-week combined baseline period were randomized 1:1 to receive VIMPAT (n=121) or placebo (n=121).

Patients were dosed on a fixed-dose regimen. Dosing was initiated at a dose of 2 mg/kg/day in patients weighing less than 50 kg or 100 mg/day in patients weighing 50 kg or more in 2 divided doses. During the titration period, VIMPAT doses were adjusted in 2 mg/kg/day increments in patients weighing less than 50 kg or 100 mg/day in patients weighing 50 kg or more at weekly intervals to achieve the target maintenance period dose of 12 mg/kg/day in patients weighing less than 30 kg, 8 mg/kg/day in patients weighing from 30 to less than 50 kg, or 400 mg/day in patients weighing 50 kg or more.

The primary efficacy endpoint (patients in the modified full analysis set: VIMPAT n=118, placebo n=121) was the time to second PGTC seizure during the 24-week treatment period (Figure 3). The risk of developing a second PGTC seizure was statistically significantly lower in VIMPAT group than in the placebo group during the 24-week treatment period (hazard ratio=0.548, 95% CI of hazard ratio: 0.381, 0.788, p-value = 0.001), with the corresponding risk reduction being 45.2%.

The key secondary efficacy endpoint was the percentage of patients not experiencing a PGTC seizure during the 24-week treatment period. The adjusted Kaplan-Meier estimates of 24-week freedom from PGTC seizures were 31.3% in VIMPAT group and 17.2% in placebo group. The adjusted difference between treatment groups was 14.1% (95% CI: 3.2, 25.1, p-value=0.011).

Figure 3 – Kaplan-Meier Analysis of Time to 2ndPGTC Seizure (Study 5) Analysis Set: Modified Full Analysis Set

The numbers at the bottom of the figure are for patients still at risk in the study at a given timepoint (i.e., the continuing patients in the study without an event or censoring prior to the timepoint).

16 HOW SUPPLIED/STORAGE AND HANDLING

16.1 How Supplied

VIMPAT (lacosamide) Tablets

- 50 mg are pink, oval, film-coated tablets debossed with "SP" on one side and "50" on the other. They are supplied as follows:
  Bottles of 60 | NDC 0131-2477-35
  Unit Dose Carton of 60 tablets [6 cards, each card contains 10 tablets] | NDC 0131-2477-60
- 100 mg are dark yellow, oval, film-coated tablets debossed with "SP" on one side and "100" on the other. They are supplied as follows:
  Bottles of 60 | NDC 0131-2478-35
  Unit Dose Carton of 60 tablets [6 cards, each card contains 10 tablets] | NDC 0131-2478-60
- 150 mg are salmon, oval, film-coated tablets debossed with "SP" on one side and "150" on the other. They are supplied as follows:
  Bottles of 60 | NDC 0131-2479-35
  Unit Dose Carton of 60 tablets [6 cards, each card contains 10 tablets] | NDC 0131-2479-60
- 200 mg are blue, oval, film-coated tablets debossed with "SP" on one side and "200" on the other. They are supplied as follows:
  Bottles of 60 | NDC 0131-2480-35
  Unit Dose Carton of 60 tablets [6 cards, each card contains 10 tablets] | NDC 0131-2480-60

VIMPAT (lacosamide) Injection

- 200 mg/20 mL is a clear, colorless sterile solution supplied in 20 mL colorless single-dose glass vials.
  200 mg/20 mL vial in cartons of 10 vials | NDC 0131-1810-67

VIMPAT (lacosamide) Oral Solution

- 10 mg/mL is a clear, colorless to yellow or yellow-brown, strawberry-flavored liquid. It is supplied as follows:
  200 mL in glass bottles | NDC 0131-5410-72

16.2 Storage and Handling

Store at 20°C to 25°C (68°F to 77°F); excursions permitted between 15°C to 30°C (59°F to 86°F). [See USP Controlled Room Temperature]

Do not freeze VIMPAT injection or oral solution. Discard any unused VIMPAT oral solution remaining after six (6) months of first opening the bottle.

17 PATIENT COUNSELING INFORMATION

Advise the patient or caregiver to read the FDA-approved patient labeling (Medication Guide). The Medication Guide accompanies the product and can also be accessed on www.vimpat.com or by calling 1-844-599-2273.

Suicidal Thinking and Behavior

Patients, their caregivers, and families should be counseled that AEDs, including VIMPAT, may increase the risk of suicidal thoughts and behavior and should be advised of the need to be alert for the emergence or worsening of symptoms of depression, any unusual changes in mood or behavior, or the emergence of suicidal thoughts, behavior, or thoughts about self-harm. Behaviors of concern should be reported immediately to healthcare providers [see Warnings and Precautions (5.1)] .

Dizziness and Ataxia

Patients should be counseled that VIMPAT use may cause dizziness, double vision, abnormal coordination and balance, and somnolence. Patients taking VIMPAT should be advised not to drive, operate complex machinery, or engage in other hazardous activities until they have become accustomed to any such effects associated with VIMPAT [see Warnings and Precautions (5.2)] .

Cardiac Rhythm and Conduction Abnormalities

Patients should be counseled that VIMPAT is associated with electrocardiographic changes that may predispose to irregular heart beat and syncope. Cardiac arrest has been reported. This risk is increased in patients with underlying cardiovascular disease, with heart conduction problems, or who are taking other medications that affect the heart. Patients should be made aware of and report cardiac signs or symptoms to their healthcare provider right away. Patients who develop syncope should lay down with raised legs and contact their health care provider [see Warnings and Precautions (5.3)] .

Drug Reaction with Eosinophilia and Systemic Symptoms (DRESS)/Multi-Organ Hypersensitivity

Patients should be aware that VIMPAT may cause serious hypersensitivity reactions affecting multiple organs such as the liver and kidney. VIMPAT should be discontinued if a serious hypersensitivity reaction is suspected. Patients should also be instructed to report promptly to their physicians any symptoms of liver toxicity (e.g., fatigue, jaundice, dark urine) [see Warnings and Precautions (5.6)] .

Pregnancy Registry

Advise patients to notify their healthcare provider if they become pregnant or intend to become pregnant during VIMPAT therapy. Encourage patients to enroll in the North American Antiepileptic Drug (NAAED) pregnancy registry if they become pregnant. This registry is collecting information about the safety of AEDs during pregnancy [see Use in Specific Populations (8.1)] .

Lactation

Advise breastfeeding women using VIMPAT to monitor infants for excess sleepiness and to seek medical care if they notice this sign [see Use in Specific Populations (8.2)].

Manufactured for: UCB, Inc. Smyrna, GA 30080

VIMPAT®is a registered trademark under license from Harris FRC Corporation and covered by one or more claims of U.S. Patent 38,551.
©2023, UCB, Inc., Smyrna, GA 30080
All rights reserved.

MEDICATION GUIDE
VIMPAT (VIM-păt)
(lacosamide)
film coated tablet, for oral use, CV
VIMPAT (VIM-păt)
(lacosamide)
injection, for intravenous use, CV
VIMPAT (VIM-păt)
(lacosamide)
oral solution, CV

Read this Medication Guide before you start taking VIMPAT and each time you get a refill. There may be new information. This Medication Guide describes important safety information about VIMPAT. This information does not take the place of talking to your healthcare provider about your medical condition or treatment.

What is the most important information I should know about VIMPAT?
Do not stop taking VIMPAT without first talking to your healthcare provider. Stopping VIMPAT suddenly can cause serious problems. Stopping seizure medicine suddenly in a patient who has epilepsy can cause seizures that will not stop (status epilepticus).
VIMPAT can cause serious side effects, including:

- Like other antiepileptic drugs, VIMPAT may cause suicidal thoughts or actions in a very small number of people, about 1 in 500.
  Call a healthcare provider right away if you have any of these symptoms, especially if they are new, worse, or worry you :

- thoughts about suicide or dying
- attempt to commit suicide
- new or worse depression
- new or worse anxiety
- feeling agitated or restless
- panic attacks

- trouble sleeping (insomnia)
- new or worse irritability
- acting aggressive, being angry, or violent
- acting on dangerous impulses
- an extreme increase in activity and talking (mania)
- other unusual changes in behavior or mood

How can I watch for early symptoms of suicidal thoughts and actions?

- Pay attention to any changes, especially sudden changes, in mood, behaviors, thoughts, or feelings.
- Keep all follow-up visits with your healthcare provider as scheduled.
- Call your healthcare provider between visits as needed, especially if you are worried about symptoms.
- Suicidal thoughts or actions can be caused by things other than medicines. If you have suicidal thoughts or actions, your healthcare provider may check for other causes.

- VIMPAT may cause you to feel dizzy, have double vision, feel sleepy, or have problems with coordination and walking. Do not drive, operate heavy machinery, or do other dangerous activities until you know how VIMPAT affects you.
- VIMPAT may cause you to have an irregular heartbeat or may cause you to faint. In rare cases, cardiac arrest has been reported. Call your healthcare provider right away if you:

- have a fast, slow, or pounding heartbeat or feel your heart skip a beat
- have shortness of breath
- have chest pain

- feel lightheaded
- fainted or if you feel like you are going to faint

If you have fainted or feel like you are going to faint you should lay down with your legs raised.

- VIMPAT is a federally controlled substance (CV) because it can be abused or lead to drug dependence. Keep your VIMPAT in a safe place, to protect it from theft. Never give your VIMPAT to anyone else, because it may harm them. Selling or giving away this medicine is against the law.

What is VIMPAT?
VIMPAT is a prescription medicine used:

- to treat partial-onset seizures in people 1 month of age and older.
- with other medicines to treat primary generalized tonic-clonic seizures in people 4 years of age and older.

It is not known if VIMPAT is safe and effective for partial-onset seizures in children under 1 month of age or for primary generalized tonic-clonic seizures in children under 4 years of age.

What should I tell my healthcare provider before taking VIMPAT?
Before you take VIMPAT, tell your healthcare provider about all of your medical conditions, including if you :

- have or have had depression, mood problems or suicidal thoughts or behavior.
- have heart problems.
- have kidney problems.
- have liver problems.
- have abused prescription medicines, street drugs or alcohol in the past.
- are pregnant or plan to become pregnant. It is not known if VIMPAT can harm your unborn baby. Tell your healthcare provider right away if you become pregnant while taking VIMPAT. You and your healthcare provider will decide if you should take VIMPAT while you are pregnant.
  - If you become pregnant while taking VIMPAT, talk to your healthcare provider about registering with the North American Antiepileptic Drug Pregnancy Registry. You can enroll in this registry by calling 1-888-233-2334. The purpose of this registry is to collect information about the safety of antiepileptic medicine during pregnancy.
- are breastfeeding or plan to breastfeed. VIMPAT passes into breast milk.
  - Breastfeeding during treatment with VIMPAT may cause your baby to have more sleepiness than normal. If this happens, contact your baby's healthcare provider.
  - Talk to your healthcare provider about the best way to feed your baby if you take VIMPAT.

Tell your healthcare provider about all the medicines you take, including prescription and over-the-counter medicines, vitamins, and herbal supplements.
Taking VIMPAT with certain other medicines may cause side effects or affect how well they work. Do not start or stop other medicines without talking to your healthcare provider. Know the medicines you take. Keep a list of them and show it to your healthcare provider and pharmacist each time you get a new medicine.

How should I take VIMPAT?

- Take VIMPAT exactly as your healthcare provider tells you.
- Your healthcare provider will tell you how much VIMPAT to take and when to take it.
- Your healthcare provider may change your dose if needed.
- Do not stop VIMPAT without first talking to a healthcare provider. Stopping VIMPAT suddenly in a patient who has epilepsy can cause seizures that will not stop (status epilepticus).
- VIMPAT may be taken with or without food.
- Swallow VIMPAT tablets whole with liquid. Do not cut VIMPAT tablets.
- If your healthcare provider has prescribed VIMPAT oral solution, be sure to ask your pharmacist for a medicine dropper or medicine cup to help you measure the correct amount of VIMPAT oral solution. Do not use a household teaspoon. Ask your pharmacist for instructions on how to use the measuring device the right way.
- If you take too much VIMPAT, call your healthcare provider or local Poison Control Center right away.

What should I avoid while taking VIMPAT?
Do not drive, operate heavy machinery, or do other dangerous activities until you know how VIMPAT affects you. VIMPAT may cause you to feel dizzy, have double vision, feel sleepy, or have problems with coordination and walking.

What are the possible side effects of VIMPAT?

- See " What is the most important information I should know about VIMPAT?"

VIMPAT may cause other serious side effects including:

- A serious allergic reaction that may affect your skin or other parts of your body such as your liver or blood cells. Call your healthcare provider right away if you have:

- a skin rash, hives
- fever or swollen glands that do not go away
- shortness of breath
- tiredness (fatigue)

- swelling of the legs
- yellowing of the skin or whites of the eyes
- dark urine

The most common side effects of VIMPAT include:

- double vision
- headache
- dizziness

- nausea
- sleepiness

These are not all of the possible side effects of VIMPAT. For more information ask your healthcare provider or pharmacist. Tell your healthcare provider about any side effect that bothers you or that does not go away. Call your doctor for medical advice about side effects. You may report side effects to FDA at 1-800-FDA-1088.

How should I store VIMPAT?

- Store VIMPAT at room temperature between 68ºF to 77ºF (20ºC to 25ºC).
- Do not freeze VIMPAT injection or oral solution.
- Throw away any unused VIMPAT oral solution 6 months after you first open the bottle.

Keep VIMPAT and all medicines out of the reach of children.

General Information about the safe and effective use of VIMPAT.
Medicines are sometimes prescribed for purposes other than those listed in a Medication Guide. Do not use VIMPAT for a condition for which it was not prescribed. Do not give VIMPAT to other people, even if they have the same symptoms that you have. It may harm them.
This Medication Guide summarizes the most important information about VIMPAT. If you would like more information, talk with your healthcare provider. You can ask your pharmacist or healthcare provider for information about VIMPAT that is written for health professionals.

What are the ingredients in VIMPAT?
Active ingredient : lacosamide
Tablet inactive ingredients: colloidal silicon dioxide, crospovidone, hydroxypropylcellulose, magnesium stearate, microcrystalline cellulose, polyethylene glycol, polyvinyl alcohol, talc, titanium dioxide and additional ingredients listed below:

- 50 mg tablets: red iron oxide, black iron oxide, FD&C Blue #2/indigo carmine aluminum lake
- 100 mg tablets: yellow iron oxide
- 150 mg tablets: yellow iron oxide, red iron oxide, black iron oxide
- 200 mg tablets: FD&C Blue #2/indigo carmine aluminum lake

Injection inactive ingredients: sodium chloride (7.62 mg/mL), water for injection, hydrochloric acid (for pH adjustment)
Oral solution inactive ingredients: purified water, sorbitol solution, glycerin, polyethylene glycol, carboxymethylcellulose sodium, acesulfame potassium, methylparaben, flavoring (including natural and artificial flavors, propylene glycol, aspartame, and maltol), anhydrous citric acid and sodium chloride.
Manufactured for: UCB, Inc. Smyrna, GA 30080
VIMPAT® is a registered trademark under license from Harris FRC Corporation and covered by one or more claims of U.S. Patent 38,551.
For more information, go to www.vimpat.com or call 1-844-599-2273.

This Medication Guide has been approved by the U.S. Food and Drug Administration

Revised: 9/2022

PRINCIPAL DISPLAY PANEL - 50 mg Tablet Blister Card Carton

NDC 0131-2477-60
Rx only

VIMPAT®
(lacosamide) tablets CV

50 mg

ATTENTION PHARMACIST:
Each patient is required to receive
the accompanying Medication Guide.

Unit Dose
60 Tablets
(6 cards, each card
contains 10 tablets)

Manufactured for:
UCB, Inc.
Smyrna, GA 30080

PRINCIPAL DISPLAY PANEL - 100 mg Tablet Blister Card Carton

NDC 0131-2478-60
Rx only

VIMPAT®
(lacosamide) tablets CV

100 mg

ATTENTION PHARMACIST:
Each patient is required to receive
the accompanying Medication Guide.

Unit Dose
60 Tablets
(6 cards, each card
contains 10 tablets)

Manufactured for:
UCB, Inc.
Smyrna, GA 30080

PRINCIPAL DISPLAY PANEL - 150 mg Tablet Blister Card Carton

NDC 0131-2479-60
Rx only

VIMPAT®
(lacosamide) tablets CV

150 mg

ATTENTION PHARMACIST:
Each patient is required to receive
the accompanying Medication Guide.

Unit Dose
60 Tablets
(6 cards, each card
contains 10 tablets)

Manufactured for:
UCB, Inc.
Smyrna, GA 30080

PRINCIPAL DISPLAY PANEL - 200 mg Tablet Blister Card Carton

NDC 0131-2480-60
Rx only

VIMPAT®
(lacosamide) tablets CV

200 mg

ATTENTION PHARMACIST:
Each patient is required to receive
the accompanying Medication Guide.

Unit Dose
60 Tablets
(6 cards, each card
contains 10 tablets)

Manufactured for:
UCB, Inc.
Smyrna, GA 30080

PRINCIPAL DISPLAY PANEL - 20 mL Vial Carton

NDC 0131-1810-67
Rx Only

Intravenous Use Only
10 single-dose vials

VIMPAT®
(lacosamide) injection CV

200 mg /20 mL
(10 mg/mL)

Manufactured for:
UCB, Inc.
Smyrna, GA 30080

PRINCIPAL DISPLAY PANEL - 200 mL Bottle Label - NDC 0131-5410-72

NDC 0131-5410-72

VIMPAT®
(lacosamide) oral solution CV

10 mg / mL

Rx only

ATTENTION PHARMACIST:
Each patient is required to receive the
accompanying Medication Guide.

Manufactured for:
UCB, Inc.
Smyrna, GA 30080

200 mL